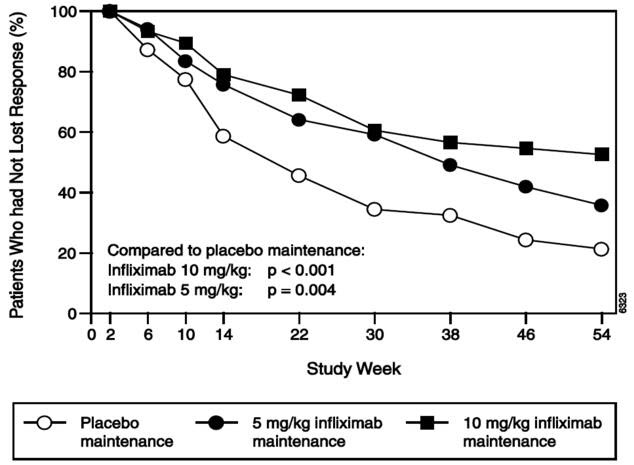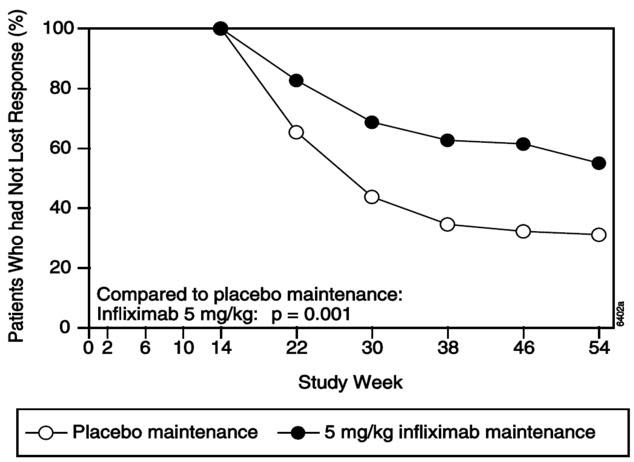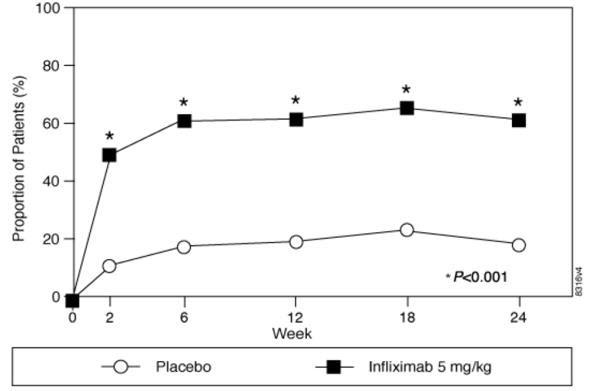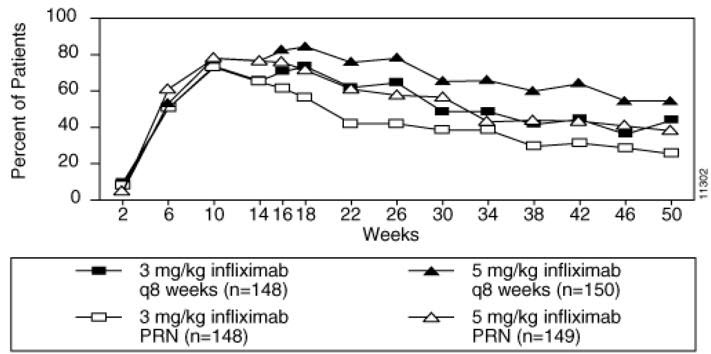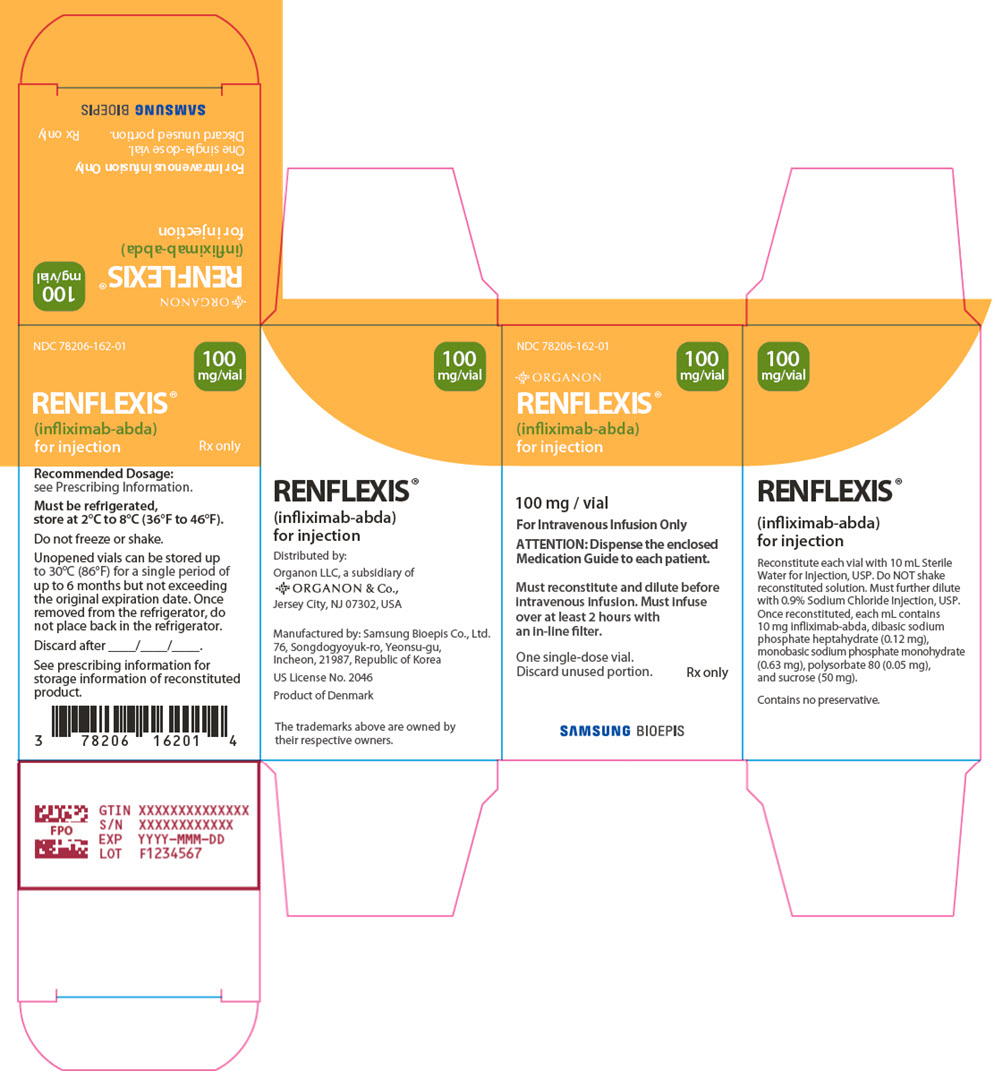 DRUG LABEL: Renflexis
NDC: 78206-162 | Form: INJECTION, POWDER, LYOPHILIZED, FOR SOLUTION
Manufacturer: Organon LLC
Category: prescription | Type: HUMAN PRESCRIPTION DRUG LABEL
Date: 20251105

ACTIVE INGREDIENTS: infliximab 100 mg/1 1
INACTIVE INGREDIENTS: sucrose 500 mg/1 1; polysorbate 80 0.5 mg/1 1; sodium phosphate, monobasic, monohydrate 6.3 mg/1 1; sodium phosphate, dibasic, heptahydrate 1.2 mg/1 1

HIGHLIGHTS OF PRESCRIBING INFORMATION

These highlights do not include all the information needed to use RENFLEXIS® safely and effectively. See full prescribing information for RENFLEXIS.
RENFLEXIS (infliximab-abda) for injection, for intravenous use
Initial U.S. Approval: 2017
RENFLEXIS (infliximab-abda) is biosimilar [Biosimilar means that the biological product is approved based on data demonstrating that it is highly similar to an FDA-approved biological product, known as a reference product, and that there are no clinically meaningful differences between the biosimilar product and the reference product. Biosimilarity of RENFLEXIS has been demonstrated for the condition(s) of use (e.g. indication(s), dosing regimen(s)), strength(s), dosage form(s), and route(s) of administration described in its Full Prescribing Information.] to REMICADE (infliximab).

WARNING: SERIOUS INFECTIONS and MALIGNANCY

See full prescribing information for complete boxed warning.

- Increased risk of serious infections leading to hospitalization or death, including tuberculosis (TB), bacterial sepsis, invasive fungal infections (such as histoplasmosis) and infections due to other opportunistic pathogens. (5.1)
- Discontinue RENFLEXIS if a patient develops a serious infection.
- Perform test for latent TB; if positive, start treatment for TB prior to starting RENFLEXIS. Monitor all patients for active TB during treatment, even if initial latent TB test is negative. (5.1)
- Lymphoma and other malignancies, some fatal, have been reported in children and adolescent patients treated with tumor necrosis factor (TNF) blockers, including infliximab products. (5.2)
- Postmarketing cases of fatal hepatosplenic T-cell lymphoma (HSTCL) have been reported in patients treated with TNF blockers including infliximab products. Almost all had received azathioprine or 6- mercaptopurine concomitantly with a TNF blocker at or prior to diagnosis. The majority of cases were reported in patients with Crohn's disease or ulcerative colitis, most of whom were adolescent or young adult males. (5.2)

1 INDICATIONS AND USAGE

RENFLEXIS is a tumor necrosis factor (TNF) blocker indicated for:

- Crohn's Disease:
  - reducing signs and symptoms and inducing and maintaining clinical remission in adult patients with moderately to severely active disease who have had an inadequate response to conventional therapy. (1.1)
  - reducing the number of draining enterocutaneous and rectovaginal fistulas and maintaining fistula closure in adult patients with fistulizing disease. (1.1)
- Pediatric Crohn's Disease:
  - reducing signs and symptoms and inducing and maintaining clinical remission in pediatric patients 6 years of age and older with moderately to severely active disease who have had an inadequate response to conventional therapy. (1.2)
- Ulcerative Colitis:
  - reducing signs and symptoms, inducing and maintaining clinical remission and mucosal healing, and eliminating corticosteroid use in adult patients with moderately to severely active disease who have had an inadequate response to conventional therapy. (1.3)
- Pediatric Ulcerative Colitis:
  - reducing signs and symptoms and inducing and maintaining clinical remission in pediatric patients 6 years of age and older with moderately to severely active disease who have had an inadequate response to conventional therapy. (1.4)
- Rheumatoid Arthritis in combination with methotrexate:
  - reducing signs and symptoms, inhibiting the progression of structural damage, and improving physical function in adult patients with moderately to severely active disease. (1.5)
- Ankylosing Spondylitis:
  - reducing signs and symptoms in adult patients with active disease. (1.6)
- Psoriatic Arthritis:
  - reducing signs and symptoms of active arthritis, inhibiting the progression of structural damage, and improving physical function in adult patients. (1.7)
- Plaque Psoriasis:
  - treatment of adult patients with chronic severe (i.e., extensive and/or disabling) plaque psoriasis who are candidates for systemic therapy and when other systemic therapies are medically less appropriate. (1.8)

2 DOSAGE AND ADMINISTRATION

- Prior to treatment, ensure appropriate personnel and medication are available to treat reactions (e.g., hypersensitivity) that occur during infusion and shortly after infusion. (2.10)
- RENFLEXIS is administered by intravenous infusion for at least 2 hours with an in-line filter. (2.11)
- Crohn's Disease:
  - 5 mg/kg at 0, 2 and 6 weeks, then every 8 weeks. Some adult patients who initially respond to treatment may benefit from increasing the dose to 10 mg/kg every 8 weeks if they later lose their response. (2.1)
- Pediatric Crohn's Disease (≥ 6 years old):
  - 5 mg/kg at 0, 2 and 6 weeks, then every 8 weeks. (2.2)
- Ulcerative Colitis:
  - 5 mg/kg at 0, 2 and 6 weeks, then every 8 weeks. (2.3)
- Pediatric Ulcerative Colitis (≥ 6 years old):
  - 5 mg/kg at 0, 2 and 6 weeks, then every 8 weeks. (2.4)
- Rheumatoid Arthritis:
  - In conjunction with methotrexate, 3 mg/kg at 0, 2 and 6 weeks, then every 8 weeks. Some patients may benefit from increasing the dose up to 10 mg/kg every 8 weeks or treating as often as every 4 weeks. (2.5)
- Ankylosing Spondylitis:
  - 5 mg/kg at 0, 2 and 6 weeks, then every 6 weeks. (2.6)
- Psoriatic Arthritis and Plaque Psoriasis:
  - 5 mg/kg at 0, 2 and 6 weeks, then every 8 weeks. (2.7, 2.8)

3 DOSAGE FORMS AND STRENGTHS

For injection: 100 mg of infliximab-abda as a lyophilized powder in a single-dose vial for reconstitution and dilution. (2.11, 3)

4 CONTRAINDICATIONS

- RENFLEXIS doses >5 mg/kg in moderate or severe heart failure. (4)
- Previous severe hypersensitivity reaction to infliximab products or any inactive ingredients of RENFLEXIS or to any murine proteins. (4)

5 WARNINGS AND PRECAUTIONS

- Serious infections – do not give RENFLEXIS during an active infection. If an infection develops, monitor carefully and stop RENFLEXIS if infection becomes serious. (5.1)
- Invasive fungal infections – for patients who develop a systemic illness on RENFLEXIS, consider empiric antifungal therapy for those who reside or travel to regions where mycoses are endemic. (5.1)
- Malignancies – the incidence of malignancies, including invasive cervical cancer and lymphoma, was greater in infliximab- treated patients than in controls. Due to the risk of HSTCL carefully assess the risk/benefit especially if the patient has Crohn's disease or ulcerative colitis, is male, and is receiving azathioprine or 6-mercaptopurine treatment. (5.2)
- Hepatitis B virus reactivation – test for HBV infection before starting RENFLEXIS. Monitor HBV carriers during and several months after therapy. If reactivation occurs, stop RENFLEXIS and begin anti-viral therapy. (5.3)
- Hepatotoxicity – severe hepatic reactions, some fatal or necessitating liver transplantation. Stop RENFLEXIS in cases of jaundice and/or marked liver enzyme elevations. (5.4)
- Heart failure – new onset or worsening symptoms may occur. (4, 5.5)
- Cytopenias – advise patients to seek immediate medical attention if signs and symptoms develop, and consider stopping RENFLEXIS. (5.6)
- Hypersensitivity – serious infusion reactions including anaphylaxis or serum sickness-like reactions may occur. (5.7)
- Cardiovascular and Cerebrovascular Reactions – Cerebrovascular accidents, myocardial infarctions (some fatal), and arrhythmias have been reported during and within 24 hours of initiation of infliximab product infusion. Monitor patients during RENFLEXIS infusion and if serious reaction occurs, discontinue infusion. (5.8)
- Demyelinating disease – exacerbation or new onset may occur. (5.9)
- Lupus-like syndrome – stop RENFLEXIS if syndrome develops. (5.12)
- Vaccinations and Use of Live Vaccines/Therapeutic Infectious Agents – Prior to initiating RENFLEXIS bring pediatric and adult patients up to date with all vaccinations. Live vaccines or therapeutic infectious agents should not be given with RENFLEXIS. At least a six month waiting period following birth is recommended before the administration of live vaccines to infants exposed in utero to infliximab products. (5.13)

6 ADVERSE REACTIONS

Most common adverse reactions (>10%) – infections (e.g. upper respiratory, sinusitis, and pharyngitis), infusion-related reactions, headache, and abdominal pain. (6.1)

To report SUSPECTED ADVERSE REACTIONS, contact Organon LLC, a subsidiary of Organon & Co., at 1-844-674-3200 or FDA at 1-800-FDA-1088 or www.fda.gov/medwatch.

7 DRUG INTERACTIONS

Other Biological Products – increased risk of serious infections. (7.1)

FULL PRESCRIBING INFORMATION

WARNING: SERIOUS INFECTIONS and MALIGNANCY

SERIOUS INFECTIONS

Patients treated with infliximab products are at increased risk for developing serious infections that may lead to hospitalization or death [see Warnings and Precautions (5.1) and Adverse Reactions (6.1)]. Most patients who developed these infections were taking concomitant immunosuppressants such as methotrexate or corticosteroids.

RENFLEXIS should be discontinued if a patient develops a serious infection or sepsis.

Reported infections include:

- Active tuberculosis, including reactivation of latent tuberculosis. Patients with tuberculosis have frequently presented with disseminated or extrapulmonary disease. Patients should be tested for latent tuberculosis before RENFLEXIS use and during therapy. Treatment for latent infection should be initiated prior to RENFLEXIS use.
- Invasive fungal infections, including histoplasmosis, coccidioidomycosis, candidiasis, aspergillosis, blastomycosis, and pneumocystosis. Patients with histoplasmosis or other invasive fungal infections may present with disseminated, rather than localized, disease. Antigen and antibody testing for histoplasmosis may be negative in some patients with active infection. Empiric anti-fungal therapy should be considered in patients at risk for invasive fungal infections who develop severe systemic illness.
- Bacterial, viral and other infections due to opportunistic pathogens, including Legionella and Listeria.

The risks and benefits of treatment with RENFLEXIS should be carefully considered prior to initiating therapy in patients with chronic or recurrent infection.

Patients should be closely monitored for the development of signs and symptoms of infection during and after treatment with RENFLEXIS, including the possible development of tuberculosis in patients who tested negative for latent tuberculosis infection prior to initiating therapy.

MALIGNANCY

Lymphoma and other malignancies, some fatal, have been reported in children and adolescent patients treated with TNF blockers, including infliximab products [see Warnings and Precautions (5.2)].

Postmarketing cases of hepatosplenic T-cell lymphoma (HSTCL), a rare type of T-cell lymphoma, have been reported in patients treated with TNF blockers including infliximab products. These cases have had a very aggressive disease course and have been fatal. Almost all patients had received treatment with azathioprine or 6-mercaptopurine concomitantly with a TNF blocker at or prior to diagnosis. The majority of reported cases have occurred in patients with Crohn's disease or ulcerative colitis and most were in adolescent and young adult males.

1 INDICATIONS AND USAGE

1.1 Crohn's Disease

RENFLEXIS is indicated for:

- reducing signs and symptoms and inducing and maintaining clinical remission in adult patients with moderately to severely active Crohn's disease (CD) who have had an inadequate response to conventional therapy.
- reducing the number of draining enterocutaneous and rectovaginal fistulas and maintaining fistula closure in adult patients with fistulizing CD.

1.2 Pediatric Crohn's Disease

RENFLEXIS is indicated for reducing signs and symptoms and inducing and maintaining clinical remission in pediatric patients 6 years of age and older with moderately to severely active CD who have had an inadequate response to conventional therapy.

1.3 Ulcerative Colitis

RENFLEXIS is indicated for reducing signs and symptoms, inducing and maintaining clinical remission and mucosal healing, and eliminating corticosteroid use in adult patients with moderately to severely active ulcerative colitis (UC) who have had an inadequate response to conventional therapy.

1.4 Pediatric Ulcerative Colitis

RENFLEXIS is indicated for reducing signs and symptoms and inducing and maintaining clinical remission in pediatric patients 6 years of age and older with moderately to severely active UC who have had an inadequate response to conventional therapy.

1.5 Rheumatoid Arthritis

RENFLEXIS, in combination with methotrexate, is indicated for reducing signs and symptoms, inhibiting the progression of structural damage, and improving physical function in adult patients with moderately to severely active rheumatoid arthritis (RA).

1.6 Ankylosing Spondylitis

RENFLEXIS is indicated for reducing signs and symptoms in adult patients with active ankylosing spondylitis (AS).

1.7 Psoriatic Arthritis

RENFLEXIS is indicated for reducing signs and symptoms of active arthritis, inhibiting the progression of structural damage, and improving physical function in adult patients with psoriatic arthritis (PsA).

1.8 Plaque Psoriasis

RENFLEXIS is indicated for the treatment of adult patients with chronic severe (i.e., extensive and/or disabling) plaque psoriasis (Ps) who are candidates for systemic therapy and when other systemic therapies are medically less appropriate. RENFLEXIS should only be administered to patients who will be closely monitored and have regular follow-up visits with a physician [see Boxed Warning and Warnings and Precautions (5)].

2 DOSAGE AND ADMINISTRATION

2.1 Dosage in Adult Crohn's Disease

The recommended dosage of RENFLEXIS is 5 mg/kg given as an intravenous induction regimen at 0, 2 and 6 weeks followed by a maintenance regimen of 5 mg/kg every 8 weeks thereafter for the treatment of adults with moderately to severely active CD or fistulizing CD. For adult patients who respond and then lose their response, consideration may be given to treatment with 10 mg/kg every 8 weeks. Patients who do not respond by Week 14 are unlikely to respond with continued dosing and consideration should be given to discontinue RENFLEXIS in these patients.

2.2 Dosage in Pediatric Crohn's Disease

The recommended dosage of RENFLEXIS for pediatric patients 6 years and older with moderately to severely active CD is 5 mg/kg given as an intravenous induction regimen at 0, 2 and 6 weeks followed by a maintenance regimen of 5 mg/kg every 8 weeks.

2.3 Dosage in Adult Ulcerative Colitis

The recommended dosage of RENFLEXIS is 5 mg/kg given as an intravenous induction regimen at 0, 2 and 6 weeks followed by a maintenance regimen of 5 mg/kg every 8 weeks thereafter for the treatment of adult patients with moderately to severely active UC.

2.4 Dosage in Pediatric Ulcerative Colitis

The recommended dosage of RENFLEXIS for pediatric patients 6 years and older with moderately to severely active UC is 5 mg/kg given as an intravenous induction regimen at 0, 2 and 6 weeks followed by a maintenance regimen of 5 mg/kg every 8 weeks.

2.5 Dosage in Rheumatoid Arthritis

The recommended dosage of RENFLEXIS is 3 mg/kg given as an intravenous induction regimen at 0, 2 and 6 weeks followed by a maintenance regimen of 3 mg/kg every 8 weeks thereafter for the treatment of moderately to severely active RA. RENFLEXIS should be given in combination with methotrexate. For patients who have an incomplete response, consideration may be given to adjusting the dosage up to 10 mg/kg every 8 weeks or treating as often as every 4 weeks bearing in mind that risk of serious infections is increased at higher doses per infusion or more frequent dosing [see Adverse Reactions (6.1)].

2.6 Dosage in Ankylosing Spondylitis

The recommended dosage of RENFLEXIS is 5 mg/kg given as an intravenous induction regimen at 0, 2 and 6 weeks followed by a maintenance regimen of 5 mg/kg every 6 weeks thereafter for the treatment of active AS.

2.7 Dosage in Psoriatic Arthritis

The recommended dosage of RENFLEXIS is 5 mg/kg given as an intravenous induction regimen at 0, 2 and 6 weeks followed by a maintenance regimen of 5 mg/kg every 8 weeks thereafter for the treatment of PsA. RENFLEXIS can be used with or without methotrexate.

2.8 Dosage in Plaque Psoriasis

The recommended dosage of RENFLEXIS in adult patients is 5 mg/kg given as an intravenous induction regimen at 0, 2 and 6 weeks followed by a maintenance regimen of 5 mg/kg every 8 weeks thereafter for the treatment of chronic severe (i.e., extensive and/or disabling) Ps.

2.9 Assessment for Latent and Active Tuberculosis

Prior to initiating RENFLEXIS and periodically during therapy, patients should be evaluated for active tuberculosis and tested for latent infection [see Warnings and Precautions (5.1)].

2.10 Administration Instructions Regarding Infusion Reactions

Prior to treatment, ensure appropriate personnel and medication are available to treat reactions (e.g., hypersensitivity, other reactions) that occur during infusion and shortly after infusion. Prior to infusion with RENFLEXIS, patients may be premedicated with histamine-1 receptor antagonists, histamine-2 receptor antagonists, acetaminophen, and/or corticosteroids [see Warnings and Precautions (5.7)].

For mild to moderate reactions during the infusion, consider slowing or stopping the infusion. Upon resolution of these reactions, may reinitiate at a lower infusion rate and/or with histamine-1 receptor antagonists, histamine-2 receptor antagonists, acetaminophen, and/or corticosteroids. Discontinue the infusion if the mild to moderate reactions reoccur.

Discontinue the infusion if severe hypersensitivity reactions occur during the infusion.

2.11 Reconstitution, Dilution, and Administration Instructions

RENFLEXIS is intended for use under the guidance and supervision of a healthcare provider. The supplied lyophilized powder must be reconstituted and diluted prior to administration. The infusion solution should be prepared and administered by a trained medical professional using aseptic technique by the following procedure:

1. Calculate the dose, total volume of reconstituted RENFLEXIS solution required and the number of RENFLEXIS vials needed. More than one vial may be needed for a full dose.
2. Reconstitute each 100 mg RENFLEXIS vial with 10 mL of Sterile Water for Injection, USP, to obtain a concentration of 10 mg/mL, using a syringe equipped with a 21-gauge or smaller needle as follows:
  - Remove the flip-top from the vial and wipe the top with an alcohol swab.
  - Insert the syringe needle into the vial through the center of the rubber stopper and direct the stream of Sterile Water for Injection, USP, to the glass wall of the vial. Gently swirl the solution by rotating the vial to dissolve the lyophilized powder, which has a cake-like appearance. Avoid prolonged or vigorous agitation. DO NOT SHAKE. Foaming of the solution on reconstitution is not unusual.
  - Allow the reconstituted solution to stand for 5 minutes. Visually inspect the reconstituted solution for particulate matter and discoloration. The reconstituted solution should be colorless to light yellow and opalescent, and the solution may develop a few translucent particles as infliximab-abda is a protein. Do not use if the lyophilized powder has not fully dissolved or if opaque particles, discoloration, or other foreign particles are present. Do not store unused reconstituted RENFLEXIS solution.
3. Dilute the total volume of the reconstituted RENFLEXIS solution to 250 mL [For volumes greater than 250 mL, either use a larger infusion bag (e.g. 500 mL) or multiple 250 mL infusion bags to ensure that the concentration of the infusion solution does not exceed 4 mg/mL.] with sterile 0.9% Sodium Chloride Injection, USP, (do not dilute with any other diluent) as follows:
  - Withdraw a volume from the 0.9% Sodium Chloride Injection, USP, 250 mL bottle or bag equal to the total volume of reconstituted RENFLEXIS required for a dose. Slowly add the total volume of reconstituted RENFLEXIS solution from the vial(s) to the 250 mL infusion bottle or bag.
  - Discard any unused portion of the reconstituted RENFLEXIS solution remaining in the vial(s).
  - Gently invert the bag to mix the solution. The resulting infusion concentration should range between 0.4 mg/mL (minimum recommended concentration) and 4 mg/mL (maximum recommended concentration) of infliximab-abda.
4. The RENFLEXIS infusion should begin within 4 hours of reconstitution and dilution. The infusion must be administered intravenously for at least 2 hours with an infusion set with an in-line, sterile, non-pyrogenic, low-protein-binding filter (pore size of 1.2 μm or less).
  - The diluted RENFLEXIS solution may be stored at room temperature at 25 °C (77°F) for up to 4 hours, including reconstitution and dilution time.
  - If needed, the diluted RENFLEXIS solution may be stored refrigerated at 2°C to 8°C (36°F to 46°F) for up to 34 days. After removal from refrigeration, the diluted solution may be stored at room temperature at up to 25°C (77°F) for an additional 6 hours.
5. Given that the vials do not contain antibacterial preservatives, discard any unused portion of the infusion solution (do not store for reuse).

No physical biochemical compatibility studies have been conducted to evaluate the coadministration of RENFLEXIS with other agents. RENFLEXIS should not be infused concomitantly in the same intravenous line with other agents.

3 DOSAGE FORMS AND STRENGTHS

For injection: 100 mg of infliximab-abda as a white lyophilized powder in a single-dose vial for reconstitution and dilution.

4 CONTRAINDICATIONS

The use of RENFLEXIS at doses >5 mg/kg is contraindicated in patients with moderate or severe heart failure [see Warnings and Precautions (5.5) and Adverse Reactions (6.1)].

RENFLEXIS is contraindicated in patients with a previous severe hypersensitivity reaction to infliximab products or any of the inactive ingredients of RENFLEXIS or any murine proteins [severe hypersensitivity reactions have included anaphylaxis, hypotension, and serum sickness] [see Warnings and Precautions (5.7) and Adverse Reactions (6.1)].

5 WARNINGS AND PRECAUTIONS

5.1 Serious Infections

Patients treated with infliximab products are at increased risk for developing serious infections involving various organ systems and sites that may lead to hospitalization or death.

Opportunistic infections due to bacterial, mycobacterial, invasive fungal, viral, or parasitic organisms including aspergillosis, blastomycosis, candidiasis, coccidioidomycosis, cryptococcosis, histoplasmosis, legionellosis, listeriosis, pneumocystosis, salmonellosis and tuberculosis have been reported with TNF blockers. Patients have frequently presented with disseminated rather than localized disease.

Treatment with RENFLEXIS should not be initiated in patients with an active infection, including clinically important localized infections. Patients greater than 65 years of age, patients with co-morbid conditions and/or patients taking concomitant immunosuppressants such as corticosteroids or methotrexate may be at greater risk of infection. The risks and benefits of treatment should be considered prior to initiating therapy in patients:

- with chronic or recurrent infection;
- who have been exposed to tuberculosis;
- with a history of an opportunistic infection;
- who have resided or traveled in areas of endemic tuberculosis or endemic mycoses, such as histoplasmosis, coccidioidomycosis, or blastomycosis; or
- with underlying conditions that may predispose them to infection.

Tuberculosis

Cases of reactivation of tuberculosis or new tuberculosis infections have been observed in patients receiving infliximab products, including patients who have previously received treatment for latent or active tuberculosis. Cases of active tuberculosis have also occurred in patients being treated with infliximab products during treatment for latent tuberculosis.

Patients should be evaluated for tuberculosis risk factors and tested for latent infection prior to initiating RENFLEXIS and periodically during therapy. Treatment of latent tuberculosis infection prior to therapy with TNF blockers has been shown to reduce the risk of tuberculosis reactivation during therapy. Induration of 5 mm or greater with tuberculin skin testing should be considered a positive test result when assessing if treatment for latent tuberculosis is needed prior to initiating RENFLEXIS, even for patients previously vaccinated with Bacille Calmette-Guérin (BCG).

Anti-tuberculosis therapy should also be considered prior to initiation of RENFLEXIS in patients with a past history of latent or active tuberculosis in whom an adequate course of treatment cannot be confirmed, and for patients with a negative test for latent tuberculosis but having risk factors for tuberculosis infection. Consultation with a physician with expertise in the treatment of tuberculosis is recommended to aid in the decision whether initiating anti-tuberculosis therapy is appropriate for an individual patient.

Tuberculosis should be strongly considered in patients who develop a new infection during RENFLEXIS treatment, especially in patients who have previously or recently traveled to countries with a high prevalence of tuberculosis, or who have had close contact with a person with active tuberculosis.

Monitoring

Patients should be closely monitored for the development of signs and symptoms of infection during and after treatment with RENFLEXIS, including the development of tuberculosis in patients who tested negative for latent tuberculosis infection prior to initiating therapy. Tests for latent tuberculosis infection may also be falsely negative while on therapy with RENFLEXIS.

RENFLEXIS should be discontinued if a patient develops a serious infection or sepsis. A patient who develops a new infection during treatment with RENFLEXIS should be closely monitored, undergo a prompt and complete diagnostic workup appropriate for an immunocompromised patient, and appropriate antimicrobial therapy should be initiated.

Invasive Fungal Infections

For patients who reside or travel in regions where mycoses are endemic, invasive fungal infection should be suspected if they develop a serious systemic illness. Appropriate empiric antifungal therapy should be considered while a diagnostic workup is being performed. Antigen and antibody testing for histoplasmosis may be negative in some patients with active infection. When feasible, the decision to administer empiric antifungal therapy in these patients should be made in consultation with a physician with expertise in the diagnosis and treatment of invasive fungal infections and should take into account both the risk for severe fungal infection and the risks of antifungal therapy.

5.2 Malignancies

Malignancies, some fatal, have been reported among children, adolescents and young adults who received treatment with TNF blockers (initiation of therapy ≤ 18 years of age), including infliximab products. Approximately half of these cases were lymphomas, including Hodgkin's and non-Hodgkin's lymphoma. The other cases represented a variety of malignancies, including rare malignancies that are usually associated with immunosuppression and malignancies that are not usually observed in children and adolescents. The malignancies occurred after a median of 30 months (range 1 to 84 months) after the first dose of TNF blocker therapy. Most of the patients were receiving concomitant immunosuppressants. These cases were reported post-marketing and are derived from a variety of sources, including registries and spontaneous postmarketing reports.

Lymphomas

In the controlled portions of clinical trials of all the TNF blockers, more cases of lymphoma have been observed among patients receiving a TNF blocker compared with control patients. In the controlled and open-label portions of infliximab clinical trials, 5 patients developed lymphomas among 5707 patients treated with infliximab (median duration of follow-up 1.0 years) vs. 0 lymphomas in 1600 control patients (median duration of follow-up 0.4 years). In RA patients, 2 lymphomas were observed for a rate of 0.08 cases per 100 patient-years of follow-up, which is approximately three-fold higher than expected in the general population. In the combined clinical trial population for RA, CD, PsA, AS, UC, and Ps, 5 lymphomas were observed for a rate of 0.10 cases per 100 patient-years of follow-up, which is approximately four-fold higher than expected in the general population. Patients with CD, RA or Ps, particularly patients with highly active disease and/or chronic exposure to immunosuppressant therapies, may be at a higher risk (up to several fold) than the general population for the development of lymphoma, even in the absence of TNF blockers. Cases of acute and chronic leukemia have been reported with postmarketing TNF blocker use in RA and other diseases. Even in the absence of TNF blocker therapy, patients with RA may be at a higher risk (approximately 2-fold) than the general population for the development of leukemia.

Hepatosplenic T-cell Lymphoma (HSTCL)

Postmarketing cases of hepatosplenic T-cell lymphoma (HSTCL), a rare type of T-cell lymphoma, have been reported in patients treated with TNF blockers including infliximab products. These cases have had a very aggressive disease course and have been fatal. Almost all patients had received treatment with the immunosuppressants azathioprine or 6-mercaptopurine concomitantly with a TNF blocker at or prior to diagnosis. The majority of reported cases have occurred in patients with CD or UC and most were in adolescent and young adult males. It is uncertain whether the occurrence of HSTCL is related to TNF blockers or TNF blockers in combination with these other immunosuppressants. When treating patients, consideration of whether to use RENFLEXIS alone or in combination with other immunosuppressants such as azathioprine or 6-mercaptopurine should take into account a possibility that there is a higher risk of HSTCL with combination therapy versus an observed increased risk of immunogenicity and hypersensitivity reactions with infliximab product monotherapy from the clinical trial data from studies with infliximab [see Warnings and Precautions (5.7) and Adverse Reactions (6.1)].

Skin Cancer

Melanoma and Merkel cell carcinoma have been reported in patients treated with TNF blocker therapy, including infliximab products [see Adverse Reactions (6.3)]. Periodic skin examination is recommended for all patients, particularly those with risk factors for skin cancer.

Cervical Cancer

A population-based retrospective cohort study using data from Swedish national health registries found a 2 to 3 fold increase in the incidence of invasive cervical cancer in women with RA treated with infliximab compared to biologics-naïve patients or the general population, particularly those over 60 years of age. A causal relationship between infliximab products and cervical cancer cannot be excluded. Periodic screening should continue in women treated with RENFLEXIS [see Adverse Reactions (6.3)].

Other Malignancies

In the controlled portions of clinical trials of some TNF blockers including infliximab products, more malignancies (excluding lymphoma and nonmelanoma skin cancer [NMSC]) have been observed in patients receiving those TNF blockers compared with control patients. During the controlled portions of infliximab trials in patients with moderately to severely active RA, CD, PsA, AS, UC, and Ps, 14 patients were diagnosed with malignancies (excluding lymphoma and NMSC) among 4019 infliximab-treated patients vs. 1 among 1597 control patients (at a rate of 0.52/100 patient-years among infliximab-treated patients vs. a rate of 0.11/100 patient-years among control patients), with median duration of follow-up 0.5 years for infliximab-treated patients and 0.4 years for control patients. Of these, the most common malignancies were breast, colorectal, and melanoma. The rate of malignancies among infliximab-treated patients was similar to that expected in the general population whereas the rate in control patients was lower than expected.

In a clinical trial exploring the use of infliximab in patients with moderate to severe chronic obstructive pulmonary disease (COPD), more malignancies, the majority of lung or head and neck origin, were reported in infliximab-treated patients compared with control patients. All patients had a history of heavy smoking [see Adverse Reactions (6.1)]. Prescribers should exercise caution when considering the use of RENFLEXIS in patients with moderate to severe COPD.

Ps patients should be monitored for nonmelanoma skin cancers (NMSCs), particularly those patients who have had prior prolonged phototherapy treatment. In the maintenance portion of clinical trials for infliximab, NMSCs were more common in patients with previous phototherapy [see Adverse Reactions (6.1)].

The potential role of TNF blockers in the development of malignancies is not known [see Adverse Reactions (6.1)]. Rates in clinical trials for infliximab cannot be compared to rates in clinical trials of other TNF blockers and may not predict rates observed in a broader patient population. Caution should be exercised in considering RENFLEXIS treatment in patients with a history of malignancy or in continuing treatment in patients who develop malignancy while receiving RENFLEXIS.

5.3 Hepatitis B Virus Reactivation

Use of TNF blockers, including infliximab products, has been associated with reactivation of hepatitis B virus (HBV) in patients who are chronic carriers of this virus. In some instances, HBV reactivation occurring in conjunction with TNF blocker therapy has been fatal. The majority of these reports have occurred in patients concomitantly receiving other medications that suppress the immune system, which may also contribute to HBV reactivation. Patients should be tested for HBV infection before initiating TNF blocker therapy, including RENFLEXIS. For patients who test positive for hepatitis B surface antigen, consultation with a physician with expertise in the treatment of hepatitis B is recommended. Adequate data are not available on the safety or efficacy of treating patients who are carriers of HBV with anti-viral therapy in conjunction with TNF blocker therapy to prevent HBV reactivation. Patients who are carriers of HBV and require treatment with TNF blockers should be closely monitored for clinical and laboratory signs of active HBV infection throughout therapy and for several months following termination of therapy. In patients who develop HBV reactivation, TNF blockers should be stopped and antiviral therapy with appropriate supportive treatment should be initiated. The safety of resuming TNF blocker therapy after HBV reactivation is controlled is not known. Therefore, prescribers should exercise caution when considering resumption of TNF blocker therapy in this situation and monitor patients closely.

5.4 Hepatotoxicity

Severe hepatic reactions, including acute liver failure, jaundice, hepatitis and cholestasis, have been reported in postmarketing data in patients receiving infliximab products. Autoimmune hepatitis has been diagnosed in some of these cases. Severe hepatic reactions occurred between 2 weeks to more than 1 year after initiation of infliximab products; elevations in hepatic aminotransferase levels were not noted prior to discovery of the liver injury in many of these cases. Some of these cases were fatal or necessitated liver transplantation. Patients with symptoms or signs of liver dysfunction should be evaluated for evidence of liver injury. If jaundice and/or marked liver enzyme elevations (e.g., ≥ 5 times the upper limit of normal) develop, RENFLEXIS should be discontinued, and a thorough investigation of the abnormality should be undertaken. In clinical trials, mild or moderate elevations of ALT and AST have been observed in patients receiving infliximab products without progression to severe hepatic injury [see Adverse Reactions (6.1)].

5.5 Heart Failure

The use of RENFLEXIS at doses >5 mg/kg is contraindicated in patients with moderate or severe heart failure. A randomized, double-blind, placebo-controlled study evaluated the use of infliximab (5 mg/kg or 10 mg/kg at Weeks 0, 2, and 6) in patients with moderate or severe heart failure [New York Heart Association (NYHA) Functional Class III/IV]. Compared to patients who received placebo, there was a higher rate of mortality and a higher risk of hospitalization at Week 28 due to heart failure in patients who received the 10 mg/kg infliximab dose, and higher rates of cardiovascular adverse events in patients who received infliximab doses of 5 mg/kg and 10 mg/kg.

There have been post-marketing reports of new onset and worsening heart failure, with and without identifiable precipitating factors (e.g., pre-existing cardiovascular disease), in patients treated with infliximab products. Some of these patients have been under 50 years of age.

If a decision is made to administer RENFLEXIS (≤ 5 mg/kg) to patients with moderate or severe heart failure or to administer RENFLEXIS (any approved dose) to patients with mild heart failure, they should be closely monitored during therapy, and RENFLEXIS should be discontinued if new or worsening symptoms of heart failure appear [see Contraindications (4) and Adverse Reactions (6.1)].

5.6 Hematologic Reactions

Cases of leukopenia, neutropenia, thrombocytopenia, and pancytopenia, some with a fatal outcome, have been reported in patients receiving infliximab products. The causal relationship to infliximab product therapy remains unclear. Although no high-risk group(s) has been identified, caution should be exercised in patients being treated with RENFLEXIS who have ongoing or a history of significant hematologic abnormalities. All patients should be advised to seek immediate medical attention if they develop signs and symptoms suggestive of blood dyscrasias or infection (e.g., persistent fever) while on RENFLEXIS. Discontinuation of RENFLEXIS therapy should be considered in patients who develop significant hematologic abnormalities.

5.7 Hypersensitivity

Infliximab products have been associated with hypersensitivity reactions that vary in their time of onset and required hospitalization in some cases. Most hypersensitivity reactions (including anaphylaxis, urticaria, dyspnea, and/or hypotension), have occurred during or within 2 hours of infliximab product infusion.

However, in some cases, serum sickness-like reactions have been observed in patients after initial therapy with infliximab products (i.e., as early as after the second dose), and when therapy with infliximab products was reinstituted following an extended period without treatment. Symptoms associated with these reactions include fever, rash, headache, sore throat, myalgias, polyarthralgias, hand and facial edema and/or dysphagia. These reactions were associated with a marked increase in antibodies to infliximab products, loss of detectable serum concentrations of infliximab products, and possible loss of drug efficacy.

RENFLEXIS should be discontinued for severe hypersensitivity reactions. Medications for the treatment of hypersensitivity reactions (e.g., acetaminophen, antihistamines, corticosteroids and/or epinephrine) should be available for immediate use in the event of a reaction [see Dosage and Administration (2.10) and Adverse Reactions (6.1)].

In RA, CD and Ps clinical trials, re-administration of infliximab after a period of no treatment resulted in a higher incidence of infusion reactions relative to regular maintenance treatment [see Adverse Reactions (6.1)]. In general, the benefit-risk of re-administration of RENFLEXIS after a period of no-treatment, especially as a re-induction regimen given at weeks 0, 2 and 6, should be carefully considered. In the case where RENFLEXIS maintenance therapy for Ps is interrupted, RENFLEXIS should be reinitiated as a single dose followed by maintenance therapy.

5.8 Cardiovascular and Cerebrovascular Reactions During and After Infusion

Serious cerebrovascular accidents, myocardial ischemia/infarction (some fatal), hypotension, hypertension, and arrhythmias have been reported during and within 24 hours of initiation of infliximab product infusion. Cases of transient visual loss have been reported during or within 2 hours of infusion of infliximab product. Monitor patients during infusion and if serious reaction occurs, discontinue infusion. Further management of reactions should be dictated by signs and symptoms [see Adverse Reactions (6)].

5.9 Neurologic Reactions

Infliximab products and other agents that inhibit TNF have been associated with CNS manifestation of systemic vasculitis, seizure and new onset or exacerbation of clinical symptoms and/or radiographic evidence of central nervous system demyelinating disorders, including multiple sclerosis and optic neuritis, and peripheral demyelinating disorders, including Guillain-Barré syndrome. Prescribers should exercise caution in considering the use of RENFLEXIS in patients with these neurologic disorders and should consider discontinuation of RENFLEXIS if these disorders develop.

5.10 Concurrent Administration with Other Biological Products

Serious infections and neutropenia were seen in clinical studies with concurrent use of anakinra and another TNF blocker, etanercept, with no added clinical benefit compared to etanercept alone. Because of the nature of the adverse reactions seen with the concurrent use of etanercept and anakinra therapy, similar toxicities may also result from the concurrent use of anakinra and other TNF blockers. Therefore, the concurrent use of RENFLEXIS and anakinra is not recommended.

In clinical studies, concurrent administration of TNF blockers and abatacept have been associated with an increased risk of infections including serious infections compared with TNF blockers alone, without increased clinical benefit. Therefore, the concurrent use of RENFLEXIS and abatacept is not recommended [see Drug Interactions (7.1)].

There is insufficient information regarding the concurrent use of infliximab products with other biological products used to treat the same conditions as RENFLEXIS. The concurrent use of RENFLEXIS with these biological products is not recommended because of the possibility of an increased risk of infection [see Drug Interactions (7.1)].

5.11 Switching Between Biological Disease-Modifying Antirheumatic Drugs (DMARDs)

Care should be taken when switching from one biologic to another, since overlapping biological activity may further increase the risk of infection.

5.12 Autoimmunity

Treatment with infliximab products may result in the formation of autoantibodies and in the development of a lupus-like syndrome. If a patient develops symptoms suggestive of a lupus-like syndrome following treatment with RENFLEXIS, treatment should be discontinued [see Adverse Reactions (6.1)].

5.13 Vaccinations and Use of Live Vaccines/Therapeutic Infectious Agents

Vaccinations

Prior to initiating RENFLEXIS in pediatric and adult patients, update vaccinations in accordance with current vaccination guidelines.

Live Vaccines and Therapeutic Infectious Agents

In patients receiving TNF blockers, limited data are available on the response to vaccination with live vaccines or on the secondary transmission of infection by live vaccines. Use of live vaccines can result in clinical infections, including disseminated infections. The concurrent administration of live vaccines with RENFLEXIS is not recommended.

Fatal outcome due to disseminated BCG infection has been reported in an infant who received a BCG vaccine after in utero exposure to infliximab products. Infliximab products are known to cross the placenta and have been detected up to 6 months following birth. At least a six month waiting period following birth is recommended before the administration of any live vaccine to infants exposed in utero to infliximab products.

Other uses of therapeutic infectious agents such as live attenuated bacteria (e.g., BCG bladder instillation for the treatment of cancer) could result in clinical infections, including disseminated infections. It is recommended that therapeutic infectious agents not be given concurrently with RENFLEXIS.

6 ADVERSE REACTIONS

6.1 Clinical Trials Experience

Because clinical trials are conducted under widely varying conditions, adverse reaction rates observed in the clinical trials of a drug cannot be directly compared to rates in the clinical trials of another drug and may not reflect the rates observed in practice.

Adverse Reactions in Adults

The data described herein reflect exposure to infliximab in 4779 adult patients (1304 patients with RA, 1106 patients with CD, 202 with AS, 293 with PsA, 484 with UC, 1373 with Ps, and 17 patients with other conditions), including 2625 patients exposed beyond 30 weeks and 374 exposed beyond 1 year. [For information on adverse reactions in pediatric patients see Adverse Reactions (6.1)]. One of the most-common reasons for discontinuation of treatment was infusion-related reactions (e.g., dyspnea, flushing, headache and rash).

Infusion-Related Reactions

Adverse Reactions During or Shortly After Infusion

An infusion reaction was defined in clinical trials as any adverse event occurring during an infusion or within 1 hour after an infusion. In all the clinical studies, approximately 20% of infliximab-treated patients experienced an infusion reaction compared with 10% of placebo-treated patients. Of infliximab-treated patients who had an infusion reaction during the induction period, 27% experienced an infusion reaction during the maintenance period. Of patients who did not have an infusion reaction during the induction period, 9% experienced an infusion reaction during the maintenance period.

Among all infliximab infusions, 3% were accompanied by nonspecific symptoms such as fever or chills, 1% were accompanied by cardiopulmonary reactions (primarily chest pain, hypotension, hypertension or dyspnea), and <1% were accompanied by pruritus, urticaria, or the combined symptoms of pruritus/urticaria and cardiopulmonary reactions. Serious infusion reactions occurred in <1% of patients and included anaphylaxis, convulsions, erythematous rash and hypotension. Approximately 3% of patients discontinued infliximab because of infusion reactions, and all patients recovered with treatment and/or discontinuation of the infusion. Infliximab infusions beyond the initial infusion were not associated with a higher incidence of reactions. The infusion reaction rates remained stable in Ps through 1 year in Ps Study I. In psoriasis Study II, the rates were variable over time and somewhat higher following the final infusion than after the initial infusion. Across the 3 Ps studies, the percent of total infusions resulting in infusion reactions (i.e., an adverse event occurring within 1 hour) was 7% in the 3 mg/kg group, 4% in the 5 mg/kg group, and 1% in the placebo group.

Patients who became positive for antibodies to infliximab were more likely (approximately two- to three-fold) to have an infusion reaction than were those who were negative. Use of concomitant immunosuppressant agents appeared to reduce the frequency of both antibodies to infliximab and infusion reactions [see Adverse Reactions (6.1) and Drug Interactions (7.3)].

Infusion Reactions Following Re-administration

In a clinical trial of patients with moderate to severe Ps designed to assess the efficacy of long-term maintenance therapy versus re-treatment with an induction regimen of infliximab following disease flare, 4% (8/219) of patients in the re-treatment induction therapy arm experienced serious infusion reactions versus < 1% (1/222) in the maintenance therapy arm. Patients enrolled in this trial did not receive any concomitant immunosuppressant therapy. In this study, the majority of serious infusion reactions occurred during the second infusion at Week 2. Symptoms included, but were not limited to, dyspnea, urticaria, facial edema, and hypotension. In all cases, infliximab treatment was discontinued and/or other treatment instituted with complete resolution of signs and symptoms.

Delayed Reactions/Reactions Following Re-administration

In Ps studies, approximately 1% of infliximab-treated patients experienced a possible delayed hypersensitivity reaction, generally reported as serum sickness or a combination of arthralgia and/or myalgia with fever and/or rash. These reactions generally occurred within 2 weeks after repeat infusion.

Infections

In infliximab clinical studies, treated infections were reported in 36% of infliximab-treated patients (average of 51 weeks of follow-up) and in 25% of placebo-treated patients (average of 37 weeks of follow-up). The infections most frequently reported were respiratory tract infections (including sinusitis, pharyngitis, and bronchitis) and urinary tract infections. Among infliximab-treated patients, serious infections included pneumonia, cellulitis, abscess, skin ulceration, sepsis, and bacterial infection. In clinical trials, 7 opportunistic infections were reported; 2 cases each of coccidioidomycosis (1 case was fatal) and histoplasmosis (1 case was fatal), and 1 case each of pneumocystosis, nocardiosis and cytomegalovirus. Tuberculosis (TB) was reported in 14 patients, 4 of whom died due to miliary tuberculosis. Other cases of TB, including disseminated TB, also have been reported post-marketing. Most of these cases of TB occurred within the first 2 months after initiation of therapy with infliximab and may reflect recrudescence of latent disease [see Warnings and Precautions (5.1)]. In the 1-year placebo-controlled studies RA I and RA II, 5.3% of patients receiving infliximab every 8 weeks with MTX developed serious infections as compared to 3.4% of placebo patients receiving MTX. Of 924 patients receiving infliximab, 1.7% developed pneumonia and 0.4% developed TB, when compared to 0.3% and 0.0% in the placebo arm respectively. In a shorter (22-week) placebo-controlled study of 1082 RA patients randomized to receive placebo, 3 mg/kg or 10 mg/kg infliximab infusions at 0, 2, and 6 weeks, followed by every 8 weeks with MTX, serious infections were more frequent in the 10 mg/kg infliximab group (5.3%) than the 3 mg/kg or placebo groups (1.7% in both). During the 54-week Crohn's II Study, 15% of patients with fistulizing CD developed a new fistula-related abscess.

In infliximab clinical studies in patients with UC, infections treated with antimicrobials were reported in 27% of infliximab-treated patients (average of 41 weeks of follow-up) and in 18% of placebo-treated patients (average 32 weeks of follow-up). The types of infections, including serious infections, reported in patients with UC were similar to those reported in other clinical studies.

The onset of serious infections may be preceded by constitutional symptoms such as fever, chills, weight loss, and fatigue. The majority of serious infections, however, may also be preceded by signs or symptoms localized to the site of the infection.

Autoantibodies/Lupus-like Syndrome

Approximately half of infliximab-treated patients in clinical trials who were antinuclear antibody (ANA) negative at baseline developed a positive ANA during the trial compared with approximately one-fifth of placebo-treated patients. Anti-dsDNA antibodies were newly detected in approximately one-fifth of infliximab-treated patients compared with 0% of placebo-treated patients. Reports of lupus and lupus-like syndromes, however, remain uncommon.

Malignancies

In controlled trials, more infliximab-treated patients developed malignancies than placebo-treated patients [see Warnings and Precautions (5.2)].

In a randomized controlled clinical trial exploring the use of infliximab in patients with moderate to severe COPD who were either current smokers or ex-smokers, 157 patients were treated with infliximab at doses similar to those used in RA and CD. Of these infliximab-treated patients, 9 developed a malignancy, including 1 lymphoma, for a rate of 7.67 cases per 100 patient-years of follow-up (median duration of follow-up 0.8 years; 95% CI 3.51-14.56). There was 1 reported malignancy among 77 control patients for a rate of 1.63 cases per 100 patient-years of follow-up (median duration of follow-up 0.8 years; 95% CI 0.04-9.10). The majority of the malignancies developed in the lung or head and neck [see Warnings and Precautions (5.2)].

Adverse Reactions in Patients with NYHA Class III/IV Heart Failure

In a randomized, double-blind study evaluating infliximab in moderate or severe heart failure (NYHA Class III/IV; left ventricular ejection fraction ≤ 35%), 150 patients were randomized to receive treatment with 3 infusions of infliximab 10 mg/kg, 5 mg/kg, or placebo, at 0, 2, and 6 weeks. Higher incidences of mortality and hospitalization due to worsening heart failure were observed in patients receiving the 10 mg/kg infliximab dose. At 1 year, 8 patients in the 10 mg/kg infliximab group had died compared with 4 deaths each in the 5 mg/kg infliximab and the placebo groups. There were trends toward increased dyspnea, hypotension, angina, and dizziness in both the 10 mg/kg and 5 mg/kg infliximab treatment groups, versus placebo. Infliximab products have not been studied in patients with mild heart failure (NYHA Class I/II) [see Contraindications (4) and Warnings and Precautions (5.5)].

Hepatotoxicity

Severe liver injury, including acute liver failure and autoimmune hepatitis, has been reported in patients receiving infliximab products [see Warnings and Precautions (5.4)]. Reactivation of hepatitis B virus has occurred in patients receiving TNF blockers, including infliximab products, who are chronic carriers of this virus [see Warnings and Precautions (5.3)].

In clinical trials in RA, CD, UC, AS, Ps, and PsA, elevations of aminotransferases were observed (ALT more common than AST) in a greater proportion of patients receiving infliximab than in controls (Table 1), both when infliximab was given as monotherapy and when it was used in combination with other immunosuppressive agents. In general, patients who developed ALT and AST elevations were asymptomatic, and the abnormalities decreased or resolved with either continuation or discontinuation of infliximab, or modification of concomitant medications.

Table 1 Proportion of Patients with Elevated ALT in Clinical Trials in Adults
 | Proportion of patients with elevated ALT
 | > 1 to < 3 × ULN |  | ≥ 3 × ULN |  | ≥ 5 × ULN
 | Placebo | Infliximab | Placebo | Infliximab | Placebo | Infliximab
Rheumatoid arthritis [Placebo patients received methotrexate while infliximab patients received both infliximab and methotrexate. Median follow-up was 58 weeks.] | 24% | 34% | 3% | 4% | < 1% | < 1%
Crohn's disease [Placebo patients in the 2 Phase 3 trials in CD received an initial dose of 5 mg/kg infliximab at study start and were on placebo in the maintenance phase. Patients who were randomized to the placebo maintenance group and then later crossed over to infliximab are included in the infliximab group in ALT analysis. Median follow-up was 54 weeks.] | 34% | 39% | 4% | 5% | 0% | 2%
Ulcerative colitis [Median follow-up was 30 weeks. Specifically, the median duration of follow-up was 30 weeks for placebo and 31 weeks for infliximab.] | 12% | 17% | 1% | 2% | < 1% | < 1%
Ankylosing spondylitis [Median follow-up was 24 weeks for the placebo group and 102 weeks for the infliximab group.] | 15% | 51% | 0% | 10% | 0% | 4%
Psoriatic arthritis [Median follow-up was 39 weeks for the infliximab group and 18 weeks for the placebo group.] | 16% | 50% | 0% | 7% | 0% | 2%
Plaque psoriasis [ALT values are obtained in 2 Phase 3 Ps studies with median follow-up of 50 weeks for infliximab and 16 weeks for placebo.] | 24% | 49% | <1% | 8% | 0% | 3%

Adverse Reactions in Psoriasis Studies

During the placebo-controlled portion across the 3 clinical trials up to Week 16, the proportion of patients who experienced at least 1 serious adverse reaction (SAE; defined as resulting in death, life threatening, requires hospitalization, or persistent or significant disability/incapacity) was 0.5% in the 3 mg/kg infliximab group, 1.9% in the placebo group, and 1.6% in the 5 mg/kg infliximab group.

Among patients in the 2 Phase 3 studies, 12.4% of patients receiving infliximab 5 mg/kg every 8 weeks through 1 year of maintenance treatment experienced at least 1 SAE in Study I. In Study II, 4.1% and 4.7% of patients receiving infliximab 3 mg/kg and 5 mg/kg every 8 weeks, respectively, through 1 year of maintenance treatment experienced at least 1 SAE.

One death due to bacterial sepsis occurred 25 days after the second infusion of 5 mg/kg infliximab. Serious infections included sepsis, and abscesses. In Study I, 2.7% of patients receiving infliximab 5 mg/kg every 8 weeks through 1 year of maintenance treatment experienced at least 1 serious infection. In Study II, 1.0% and 1.3% of patients receiving infliximab 3 mg/kg and 5 mg/kg, respectively, through 1 year of treatment experienced at least 1 serious infection. The most common serious infection (requiring hospitalization) was abscess (skin, throat, and peri-rectal) reported by 5 (0.7%) patients in the 5 mg/kg infliximab group. Two active cases of tuberculosis were reported: 6 weeks and 34 weeks after starting infliximab.

In the placebo-controlled portion of the Ps studies, 7 of 1123 patients who received infliximab at any dose were diagnosed with at least one NMSC compared to 0 of 334 patients who received placebo.

In the Ps studies, 1% (15/1373) of patients experienced serum sickness or a combination of arthralgia and/or myalgia with fever, and/or rash, usually early in the treatment course. Of these patients, 6 required hospitalization due to fever, severe myalgia, arthralgia, swollen joints, and immobility.

Other Adverse Reactions in Adults

Safety data are available from 4779 adult patients treated with infliximab, including 1304 with RA, 1106 with CD, 484 with UC, 202 with AS, 293 with PsA, 1373 with Ps and 17 with other conditions. [For information on other adverse reactions in pediatric patients, see Adverse Reactions (6.1)]. Adverse reactions reported in ≥ 5% of all patients with RA receiving 4 or more infusions are in Table 2. The types and frequencies of adverse reactions observed were similar in RA, AS, PsA, Ps, and CD patients treated with infliximab except for abdominal pain, which occurred in 26% of infliximab-treated patients with CD. In the CD studies, there were insufficient numbers and duration of follow-up for patients who never received infliximab to provide meaningful comparisons.

Table 2 Adverse Reactions that Occurred in ≥ 5% of Patients who Received ≥ 4 Infliximab Infusions for RA
 | Placebo | Infliximab
 | (n = 350) | (n = 1129)
Average weeks of follow-up | 59 weeks | 66 weeks
Upper respiratory tract infection | 25% | 32%
Nausea | 20% | 21%
Headache | 14% | 18%
Sinusitis | 8% | 14%
Diarrhea | 12% | 12%
Abdominal pain | 8% | 12%
Pharyngitis | 8% | 12%
Coughing | 8% | 12%
Bronchitis | 9% | 10%
Rash | 5% | 10%
Dyspepsia | 7% | 10%
Fatigue | 7% | 9%
Urinary tract infection | 6% | 8%
Pain | 7% | 8%
Arthralgia | 7% | 8%
Pruritus | 2% | 7%
Fever | 4% | 7%
Hypertension | 5% | 7%
Moniliasis | 3% | 5%

The most common serious adverse reactions observed in clinical trials were infections [see Adverse Reactions (6.1)]. Other serious, medically relevant adverse reactions ≥ 0.2% or clinically significant adverse reactions by body system were as follows:

Body as a whole: allergic reaction, edema

Blood: pancytopenia

Cardiovascular: hypotension

Gastrointestinal: constipation, intestinal obstruction

Central and Peripheral Nervous: dizziness

Heart Rate and Rhythm: bradycardia

Liver and Biliary: hepatitis

Metabolic and Nutritional: dehydration

Platelet, Bleeding and Clotting: thrombocytopenia

Neoplasms: lymphoma

Red Blood Cell: anemia, hemolytic anemia

Resistance Mechanism: cellulitis, sepsis, serum sickness, sarcoidosis

Respiratory: lower respiratory tract infection (including pneumonia), pleurisy, pulmonary edema

Skin and Appendages: increased sweating

Vascular (Extracardiac): thrombophlebitis

White Cell and Reticuloendothelial: leukopenia, lymphadenopathy

Adverse Reactions in Pediatric Patients

Adverse Reactions in Pediatric Patients with Crohn's Disease

There were some differences in the adverse reactions observed in the pediatric patients receiving infliximab compared to those observed in adults with CD. These differences are discussed in the following paragraphs.

The following adverse reactions were reported more commonly in 103 randomized pediatric CD patients administered 5 mg/kg infliximab through 54 weeks than in 385 adult CD patients receiving a similar treatment regimen: anemia (11%), leukopenia (9%), flushing (9%), viral infection (8%), neutropenia (7%), bone fracture (7%), bacterial infection (6%), and respiratory tract allergic reaction (6%).

Infections were reported in 56% of randomized pediatric patients in Study Peds Crohn's and in 50% of adult patients in Study Crohn's I. In Study Peds Crohn's, infections were reported more frequently for patients who received every 8-week as opposed to every 12-week infusions (74% and 38%, respectively), while serious infections were reported for 3 patients in the every 8-week and 4 patients in the every 12-week maintenance treatment group. The most commonly reported infections were upper respiratory tract infection and pharyngitis, and the most commonly reported serious infection was abscess. Pneumonia was reported for 3 patients, (2 in the every 8-week and 1 in the every 12-week maintenance treatment groups). Herpes zoster was reported for 2 patients in the every 8-week maintenance treatment group.

In Study Peds Crohn's, 18% of randomized patients experienced 1 or more infusion reactions, with no notable difference between treatment groups. Of the 112 patients in Study Peds Crohn's, there were no serious infusion reactions, and 2 patients had non-serious anaphylactoid reactions.

Elevations of ALT up to 3 times the upper limit of normal (ULN) were seen in 18% of pediatric patients in CD clinical trials; 4% had ALT elevations ≥ 3 × ULN, and 1% had elevations ≥ 5 × ULN. (Median follow-up was 53 weeks).

Adverse Reactions in Pediatric Patients with Ulcerative Colitis

Overall, the adverse reactions reported in the pediatric UC trial and adult UC (Study UC I and Study UC II) studies were generally consistent. In a pediatric UC trial, the most common adverse reactions were upper respiratory tract infection, pharyngitis, abdominal pain, fever, and headache.

Infections were reported in 31 (52%) of 60 treated patients in the pediatric UC trial and 22 (37%) required oral or parenteral antimicrobial treatment. The proportion of patients with infections in the pediatric UC trial was similar to that in the pediatric CD study (Study Peds Crohn's) but higher than the proportion in the adults' UC studies (Study UC I and Study UC II). The overall incidence of infections in the pediatric UC trial was 13/22 (59%) in the every 8 week maintenance treatment group. Upper respiratory tract infection (7/60 [12%]) and pharyngitis (5/60 [8%]) were the most frequently reported respiratory system infections. Serious infections were reported in 12% (7/60) of all treated patients.

Elevations of ALT up to 3 times the upper limit of normal (ULN) were seen in 17% (10/60) of pediatric patients in the pediatric UC trial; 7% (4/60) had ALT elevations ≥ 3 × ULN, and 2% (1/60) had elevations ≥ 5 × ULN (median follow-up was 49 weeks).

Overall, 8 of 60 (13%) treated patients experienced one or more infusion reactions, including 4 of 22 (18%) patients in the every 8-week treatment maintenance group. No serious infusion reactions were reported.

In the pediatric UC trial, 45 patients were in the 12 to 17 year age group and 15 in the 6 to 11 year age group. The numbers of patients in each subgroup are too small to make any definitive conclusions about the effect of age on safety events. There were higher proportions of patients with serious adverse events (40% vs. 18%) and discontinuation due to adverse events (40% vs. 16%) in the younger age group than in the older age group. While the proportion of patients with infections was also higher in the younger age group (60% vs. 49%), for serious infections, the proportions were similar in the two age groups (13% in the 6 to 11 year age group vs. 11% in the 12 to 17 year age group). Overall proportions of adverse reactions, including infusion reactions, were similar between the 6 to 11 and 12 to 17 year age groups (13%).

6.2 Immunogenicity

The observed incidence of anti-drug antibodies is highly dependent on the sensitivity and specificity of the assay. Differences in assay methods preclude meaningful comparisons of the incidence of anti-drug antibodies in the studies described below with the incidence of anti-drug antibodies in other studies, including those of infliximab or of other infliximab products.

Treatment with infliximab products can be associated with the development of antibodies to infliximab products. An enzyme immunoassay (EIA) method was originally used to measure anti-infliximab antibodies in clinical studies of infliximab. The EIA method is subject to interference by serum infliximab, possibly resulting in an underestimation of the rate of patient antibody formation. A separate, drug-tolerant electrochemiluminescence immunoassay (ECLIA) method for detecting antibodies to infliximab was subsequently developed and validated. This method is 60-fold more sensitive than the original EIA. With the ECLIA method, all clinical samples can be classified as either positive or negative for antibodies to infliximab without the need for the inconclusive category.

The incidence of antibodies to infliximab was based on the original EIA method in all clinical studies of infliximab except for the Phase 3 study in pediatric patients with UC where the incidence of antibodies to infliximab was detected using both the EIA and ECLIA methods.

Immunogenicity in Adult Patients

The incidence of antibodies to infliximab in patients with RA and CD given a 3-dose induction regimen followed by maintenance dosing was approximately 10% as assessed through 1 to 2 years of infliximab treatment. A higher incidence of antibodies to infliximab was observed in CD patients receiving infliximab after drug-free intervals >16 weeks. In a PsA study in which 191 patients received 5 mg/kg with or without MTX, antibodies to infliximab occurred in 15% of patients. The majority of antibody-positive patients had low titers. Antibody development was lower among RA and CD patients receiving immunosuppressant therapies such as 6-MP/AZA or MTX. Patients who were antibody-positive were more likely to have higher rates of clearance, have reduced efficacy, and to experience an infusion reaction than were patients who were antibody negative [see Adverse Reactions 6.1]. In the Ps Study II, which included both the 5 mg/kg and 3 mg/kg doses, antibodies were observed in 36% of patients treated with 5 mg/kg every 8 weeks for 1 year, and in 51% of patients treated with 3 mg/kg every 8 weeks for 1 year.

In the Ps Study III, which also included both the 5 mg/kg and 3 mg/kg doses, antibodies were observed in 20% of patients treated with 5 mg/kg induction (weeks 0, 2 and 6), and in 27% of patients treated with 3 mg/kg induction. Despite the increase in antibody formation, the infusion reaction rates in Studies I and II in patients treated with 5 mg/kg induction followed by every 8 week maintenance for 1 year and in Study III in patients treated with 5 mg/kg induction (14.1%-23.0%) and serious infusion reaction rates (<1%) were similar to those observed in other study populations. The clinical significance of apparent increased immunogenicity on efficacy and infusion reactions in Ps patients as compared to patients with other diseases treated with infliximab products over the long term is not known.

Immunogenicity in Pediatric Patients with Crohn's Disease

In Study Peds Crohn's, in which all patients received stable doses of 6-MP, AZA, or MTX, excluding inconclusive samples, 3 of 24 patients had antibodies to infliximab. Although 105 patients were tested for antibodies to infliximab, 81 patients were classified as inconclusive because they could not be ruled as negative due to assay interference by the presence of infliximab in the sample.

Immunogenicity in Pediatric Patients with Ulcerative Colitis

In the pediatric UC trial, 58 patients were evaluated for antibodies to infliximab using the EIA as well as the drug-tolerant ECLIA. With the EIA, 4 of 58 (7%) patients had antibodies to infliximab. With the ECLIA, 30 of 58 (52%) patients had antibodies to infliximab. The higher incidence of antibodies to infliximab by the ECLIA method was due to the 60-fold higher sensitivity compared to the EIA method. While EIA-positive patients generally had undetectable trough concentration of infliximab, ECLIA-positive patients could have detectable trough concentrations of infliximab because the ECLIA assay is more sensitive and drug-tolerant.

6.3 Postmarketing Experience

Adverse reactions, some with fatal outcomes, have been identified during post approval use of infliximab products in adult and pediatric patients. Because these reactions are reported voluntarily from a population of uncertain size, it is not always possible to reliably estimate their frequency or establish a causal relationship to drug exposure.

Postmarketing Adverse Reactions in Adults and Pediatric Patients

- Neutropenia [see Warnings and Precautions (5.6)], agranulocytosis (including infants exposed in utero to infliximab products), idiopathic thrombocytopenic purpura, thrombotic thrombocytopenic purpura.
- Interstitial lung disease (including pulmonary fibrosis/interstitial pneumonitis and rapidly progressive disease).
- Pericardial effusion, systemic and cutaneous vasculitis.
- Erythema multiforme, Stevens-Johnson Syndrome, toxic epidermal necrolysis, linear IgA bullous dermatosis (LABD), acute generalized exanthematous pustulosis (AGEP), worsening psoriasis (all subtypes including pustular, primarily palmoplantar), lichenoid reactions.
- Peripheral demyelinating disorders (such as Guillain-Barré syndrome, chronic inflammatory demyelinating polyneuropathy, and multifocal motor neuropathy), transverse myelitis, and neuropathies (additional neurologic reactions have also been observed) [see Warnings and Precautions (5.9)].
- Acute liver failure, jaundice, hepatitis, and cholestasis [see Warnings and Precautions (5.4)].
- Serious infections [see Warnings and Precautions (5.1)] and vaccine breakthrough infection including bovine tuberculosis (disseminated BCG infection) following vaccination in an infant exposed in utero to infliximab products [see Warnings and Precautions (5.13)].
- Malignancies, including leukemia, melanoma, Merkel cell carcinoma, and cervical cancer [see Warnings and Precautions (5.2)].
- Anaphylactic reactions, including anaphylactic shock, laryngeal/pharyngeal edema and severe bronchospasm, and seizure have been associated with administration of infliximab products.
- Transient visual loss have been reported in association with infliximab products during or within 2 hours of infusion. Cerebrovascular accidents, myocardial ischemia/infarction (some fatal), and arrhythmia occurring within 24 hours of initiation of infusion have also been reported [see Warnings and Precautions (5.8)].
- New onset immune disorders (e.g., psoriasis, rheumatoid arthritis, inflammatory bowel disease).

Postmarketing Serious Adverse Reactions in Pediatric Patients

The following serious adverse reactions have been reported in the post-marketing experience in pediatric patients: infections (some fatal) including opportunistic infections and tuberculosis, infusion reactions, hypersensitivity reactions, malignancies, including hepatosplenic T-cell lymphomas [see Boxed Warning and Warnings and Precautions (5.2)], transient hepatic enzyme abnormalities, lupus-like syndromes, and the development of autoantibodies.

7 DRUG INTERACTIONS

7.1 Other Biological Products

The combination of RENFLEXIS with other biological products used to treat the same conditions as RENFLEXIS is not recommended [see Warnings and Precautions (5.10)].

An increased risk of serious infections was seen in clinical studies of other TNF blockers used in combination with anakinra or abatacept, with no added clinical benefit. Because of the nature of the adverse reactions seen with these combinations with TNF blocker therapy, similar toxicities may also result from the combination of anakinra or abatacept with other TNF blockers. Therefore, the combination of RENFLEXIS and anakinra or abatacept is not recommended [see Warnings and Precautions (5.10)].

The concomitant use of tocilizumab with biological DMARDs such as TNF antagonists, including RENFLEXIS, should be avoided because of the possibility of increased immunosuppression and increased risk of infection.

7.2 Methotrexate and Other Concomitant Medications

Specific drug interaction studies, including interactions with methotrexate (MTX), have not been conducted. The majority of patients in RA or CD clinical studies received one or more concomitant medications. In RA, concomitant medications besides MTX were nonsteroidal anti-inflammatory agents (NSAIDs), folic acid, corticosteroids and/or narcotics. Concomitant CD medications were antibiotics, antivirals, corticosteroids, 6-MP/AZA and aminosalicylates. In PsA clinical trials, concomitant medications included MTX in approximately half of the patients as well as NSAIDs, folic acid and corticosteroids. Concomitant MTX use may decrease the incidence of anti-drug antibody production and increase infliximab product concentrations.

7.3 Immunosuppressants

Patients with CD who received immunosuppressants tended to experience fewer infusion reactions compared to patients on no immunosuppressants [see Adverse Reactions (6.1)]. Serum infliximab concentrations appeared to be unaffected by baseline use of medications for the treatment of CD including corticosteroids, antibiotics (metronidazole or ciprofloxacin) and aminosalicylates.

7.4 Cytochrome P450 Substrates

The formation of CYP450 enzymes may be suppressed by increased levels of cytokines (e.g., TNFα, IL-1, IL-6, IL-10, IFN) during chronic inflammation. Therefore, it is expected that for a molecule that antagonizes cytokine activity, such as infliximab products, the formation of CYP450 enzymes could be normalized. Upon initiation or discontinuation of RENFLEXIS in patients being treated with CYP450 substrates with a narrow therapeutic index, monitoring of the effect (e.g., warfarin) or drug concentration (e.g., cyclosporine or theophylline) is recommended and the individual dose of the drug product may be adjusted as needed.

7.5 Live Vaccines/Therapeutic Infectious Agents

It is recommended that live vaccines not be given concurrently with RENFLEXIS. It is also recommended that live vaccines not be given to infants after in utero exposure to infliximab products for at least 6 months following birth [see Warnings and Precautions (5.13)].

It is recommended that therapeutic infectious agents not be given concurrently with RENFLEXIS [see Warnings and Precautions (5.13)].

8 USE IN SPECIFIC POPULATIONS

8.1 Pregnancy

Risk Summary

Available observational studies in pregnant women exposed to infliximab products showed no increased risk of major malformations among live births as compared to those exposed to non-biologics. However, findings on other birth and maternal outcomes were not consistent across studies of different study design and conduct [see Data].

Monoclonal antibodies such as infliximab products are transferred across the placenta during the third trimester of pregnancy and may affect immune response in the in utero exposed infant [see Clinical Considerations]. Because infliximab products do not cross-react with TNFα in species other than humans and chimpanzees, animal reproduction studies have not been conducted with infliximab products. In a developmental study conducted in mice using an analogous antibody, no evidence of maternal toxicity or fetal harm was observed [see Data].

All pregnancies have a background risk of birth defect, loss, or other adverse outcomes.

The estimated background risk of major birth defects and miscarriage for the indicated populations is unknown. In the U.S. general population, the estimated background risk of major birth defects and miscarriage in clinically recognized pregnancies is 2-4% and 15-20%, respectively.

Clinical Considerations

Disease-Associated Maternal and/or Embryo/Fetal Risk

Published data suggest that there is an increased risk of adverse pregnancy outcomes in women with inflammatory bowel disease or rheumatoid arthritis associated with increased disease activity. Adverse pregnancy outcomes include preterm delivery (before 37 weeks of gestation), low birth weight (less than 2.5 kg) and small for gestational age at birth.

Fetal/Neonatal Adverse Reactions

As with other IgG antibodies, infliximab products cross the placenta. Infliximab products have been detected in the serum of infants up to 6 months following birth. Consequently, these infants may be at increased risk of infection, including disseminated infection which can become fatal. At least a six month waiting period following birth is recommended before the administration of live vaccines (e.g., BCG vaccine or other live vaccines, such as the rotavirus vaccine) to these infants [see Warnings and Precautions (5.13)]. Cases of agranulocytosis in infants exposed in utero have also been reported [see Adverse Reactions (6.3)].

Data

Human Data

Two prospective cohort studies were conducted assessing birth outcomes as well as the health status of infants up to the age of one year in women exposed to infliximab compared to non-biologic comparators including methotrexate, azathioprine, 6-mercaptopurine and systemic corticosteroids used for the treatment of similar diseases. The first study was conducted in an IBD pregnancy registry in the United States and assessed pregnancy outcomes in 294 women with inflammatory bowel disease exposed to infliximab during pregnancy compared with 515 women on a non-biologic treatment. Infliximab exposure was not associated with increased rates of major congenital malformations, miscarriage/stillbirth, infants of low birth weight, small for gestational age, or infection in the first year of life. The second study among IBD and non-IBD patients in Sweden, Finland, and Denmark compared 97, 7, and 166 women exposed to infliximab to 2,693, 2,499 and 1,268 women on non-biologic systemic therapy, respectively. In this study, comparing pooled data across the three countries, exposure to infliximab was not associated with increased rates of congenital anomalies or infant death. Infliximab in combination with immunosuppressants (mainly systemic corticosteroids and azathioprine) was associated with increased rates of preterm birth, small for gestational age, low birth weight, and infant hospitalization for infection compared with non-biologic systemic treatment. Although the study did not show any associations with infliximab monotherapy, the analyses could have been underpowered to detect an association.

There were additional methodological limitations with these studies that may account for the study findings in both studies: the concomitant use of other medications or treatments was not controlled and disease severity was not assessed; in the U.S. study, patient reported outcomes were collected without clinical validation. These methodological limitations hinder interpretation of the study results.

Animal Data

Because infliximab products do not cross-react with TNFα in species other than humans and chimpanzees, animal reproduction studies have not been conducted with infliximab products. An embryofetal development study was conducted in pregnant mice using cV1q anti-mouse TNFα, an analogous antibody that selectively inhibits the functional activity of mouse TNFα. This antibody administered in mice, during the period of organogenesis on gestation days (GDs) 6 and 12, at IV doses up to 40 mg/kg produced no evidence of maternal toxicity, fetal mortality, or structural abnormalities. Doses of 10 to 15 mg/kg in pharmacodynamic animal models with the anti-TNF analogous antibody produced maximal pharmacologic effectiveness. Analyses of fetal samples on GD 14 indicated placental transfer of the antibody and exposure of the fetuses during organogenesis. In a peri- and post-natal development study in mice, no maternal toxicity or adverse developmental effects in offspring were observed when dams were administered IV doses of 10 or 40 mg/kg of the analogous antibody on GDs 6, 12 and 18 and lactation days 3, 9 and 15.

8.2 Lactation

Risk Summary

Published literature show that infliximab is present at low levels in human milk. Systemic exposure in a breastfed infant is expected to be low because infliximab products are largely degraded in the gastrointestinal tract. A U.S. multi-center study of 168 women treated with infliximab for inflammatory bowel disease (breast milk samples obtained, n=29) showed that infants exposed to infliximab through breast milk had no increase in rates of infections and developed normally. There are no data on the effects of infliximab products on milk production. The developmental and health benefits of breastfeeding should be considered along with the mother's clinical need for RENFLEXIS and any potential adverse effects on the breastfed child from RENFLEXIS or from the underlying maternal condition.

8.4 Pediatric Use

The safety and effectiveness of RENFLEXIS have been established in pediatric patients 6 to 17 years of age for induction and maintenance treatment of CD and UC [see Dosage and Administration (2.2, 2.4) and Adverse Reactions (6.1)]. However, the safety and effectiveness of RENFLEXIS in pediatric patients <6 years of age with CD or UC have not been established. The safety and effectiveness of RENFLEXIS in the treatment of pediatric patients with Ps and juvenile rheumatoid arthritis (JRA) have not been established.

Pediatric Crohn's Disease

The safety and effectiveness of RENFLEXIS have been established for reducing signs and symptoms and inducing and maintaining clinical remission in pediatric patients 6 years of age and older with moderately to severely active CD who have had an inadequate response to conventional therapy. The use of RENFLEXIS for this indication is supported by evidence from a randomized, open-label pediatric CD study of infliximab in 112 pediatric patients aged 6 years and older [see Clinical Studies (14.2)].

Infliximab has been studied only in combination with conventional immunosuppressive therapy in pediatric CD. The longer term (greater than 1 year) safety and effectiveness of infliximab products in pediatric CD patients have not been established in clinical trials.

Postmarketing cases of HSTCL have been reported in pediatric patients treated with TNF blockers including infliximab products. Due to the risk of HSTCL, a careful risk-benefit assessment should be made when RENFLEXIS is used in combination with other immunosuppressants in pediatric CD patients [see Boxed Warning and Warnings and Precautions (5.2)].

Pediatric Ulcerative Colitis

The safety and effectiveness of RENFLEXIS for reducing signs and symptoms and inducing and maintaining clinical remission in pediatric patients aged 6 years and older with moderately to severely active UC who have had an inadequate response to conventional therapy have been established. The use of RENFLEXIS for this indication is supported by evidence from adequate and well-controlled studies of infliximab in adults with additional safety and pharmacokinetic data from an open-label pediatric UC study in 60 pediatric patients aged 6 years and older [see Dosage and Administration (2.4), Adverse Reactions (6.1), and Clinical Studies (14.4)]. The effectiveness of infliximab in inducing and maintaining mucosal healing in pediatric UC was not established. Although 41 patients had a Mayo endoscopy subscore of 0 or 1 at the Week 8 endoscopy, the induction phase was open-label and lacked a control group. Only 9 patients had an optional endoscopy at Week 54. Approximately half of the patients were on concomitant immunomodulators (AZA, 6-MP, MTX) at study start.

Due to the risk of HSTCL, a careful risk-benefit assessment should be made when RENFLEXIS is used in combination with other immunosuppressants in pediatric UC patients [see Boxed Warning and Warnings and Precautions (5.2)].

The longer term (greater than 1 year) safety and effectiveness of infliximab products in pediatric UC patients have not been established in clinical trials.

Juvenile Rheumatoid Arthritis (JRA)

The safety and effectiveness of RENFLEXIS in the treatment of pediatric patients with juvenile rheumatoid arthritis (JRA) have not been established.

The safety and efficacy of RENFLEXIS in patients with JRA is based on the evaluation of infliximab in a multicenter, randomized, placebo-controlled, double-blind study for 14 weeks, followed by a double-blind, all-active treatment extension, for a maximum of 44 weeks. Patients with active JRA between the ages of 4 and 17 years who had been treated with MTX for at least 3 months were enrolled. Concurrent use of folic acid, oral corticosteroids (≤ 0.2 mg/kg/day of prednisone or equivalent), NSAIDs, and/or disease modifying antirheumatic drugs (DMARDs) was permitted.

Doses of 3 mg/kg infliximab or placebo were administered intravenously at Weeks 0, 2 and 6. Patients randomized to placebo crossed-over to receive 6 mg/kg infliximab at Weeks 14, 16, and 20, and then every 8 weeks through Week 44. Patients who completed the study continued to receive open-label treatment with infliximab for up to 2 years in a companion extension study.

The study failed to establish the efficacy of infliximab in the treatment of JRA. Key observations in the study included a high placebo response rate and a higher rate of immunogenicity than what has been observed in adults. Additionally, a higher rate of clearance of infliximab was observed than had been observed in adults.

Population pharmacokinetic analysis showed that in pediatric patients with JRA with a body weight of up to 35 kg receiving 6 mg/kg infliximab and pediatric patients with JRA with body weight greater than 35 kg up to adult body weight receiving 3 mg/kg infliximab, the steady state area under the concentration curve (AUCss) was similar to that observed in adults receiving 3 mg/kg of infliximab.

A total of 60 patients with JRA were treated with doses of 3 mg/kg and 57 patients were treated with doses of 6 mg/kg. The proportion of patients with infusion reactions who received 3 mg/kg infliximab was 35% (21/60) over 52 weeks compared with 18% (10/57) in patients who received 6 mg/kg over 38 weeks. The most common infusion reactions reported were vomiting, fever, headache, and hypotension. In the 3 mg/kg infliximab group, 4 patients had a serious infusion reaction and 3 patients reported a possible anaphylactic reaction (2 of which were among the serious infusion reactions). In the 6 mg/kg infliximab group, 2 patients had a serious infusion reaction, 1 of whom had a possible anaphylactic reaction. Two of the 6 patients who experienced serious infusion reactions received infliximab by rapid infusion (duration of less than 2 hours). Antibodies to infliximab developed in 38% (20/53) of patients who received 3 mg/kg infliximab compared with 12% (6/49) of patients who received 6 mg/kg.

A total of 68% (41/60) of patients who received 3 mg/kg infliximab in combination with MTX experienced an infection over 52 weeks compared with 65% (37/57) of patients who received 6 mg/kg infliximab in combination with MTX over 38 weeks. The most commonly reported infections were upper respiratory tract infection and pharyngitis, and the most commonly reported serious infection was pneumonia. Other notable infections included primary varicella infection in 1 patient and herpes zoster in 1 patient.

8.5 Geriatric Use

Of the total number of infliximab-treated patients in RA and Ps clinical studies, 256 (9.6%) were 65 years old and over, while 17 (0.6%) were 75 years old and over. In these trials, no overall differences in safety or effectiveness were observed between geriatric patients (patients ≥ 65 years old) and younger adult patients (patients 18 to 65 years old). However, the incidence of serious adverse reactions in geriatric patients was higher in both infliximab and control groups compared to younger adult patients.

Of the total number of infliximab-treated patients in CD, UC, AS, and PsA clinical studies, 76 (3.2%) were 65 years old and over, while 9 (0.4%) were 75 years old and over. In the CD, UC, AS, and PsA studies, there were insufficient numbers of geriatric patients to determine whether they respond differently from younger adults.

The incidence of serious infections in infliximab-treated geriatric patients was greater than in infliximab-treated younger adult patients; therefore close monitoring of geriatric patients for the development of serious infections is recommended [see Warnings and Precautions (5.1) and Adverse Reactions (6.1)].

10 OVERDOSAGE

Single doses up to 20 mg/kg have been administered without any direct toxic effect. In case of overdosage, it is recommended that the patient be monitored for any signs or symptoms of adverse reactions or effects [see Warnings and Precautions (5)] and appropriate symptomatic treatment instituted immediately.

11 DESCRIPTION

Infliximab-abda, a tumor necrosis factor (TNF) blocker, is a chimeric IgG1κ monoclonal antibody (composed of human constant and murine variable regions). It has a molecular weight of approximately 149.1 kilodaltons. Infliximab-abda is produced by a recombinant murine myeloma cell line, SP2/0.

RENFLEXIS® (infliximab-abda) for injection is supplied as a sterile, preservative-free, white, lyophilized powder for intravenous infusion after reconstitution and dilution. Following reconstitution with 10 mL of Sterile Water for Injection, USP, the final concentration is 10 mg/mL and the resulting pH is approximately 6. Each single-dose vial contains 100 mg infliximab-abda, dibasic sodium phosphate heptahydrate (1.2 mg), monobasic sodium phosphate monohydrate (6.3 mg), polysorbate 80 (0.5 mg), and sucrose (500 mg).

12 CLINICAL PHARMACOLOGY

12.1 Mechanism of Action

Infliximab products neutralize the biological activity of TNFα by binding with high affinity to the soluble and transmembrane forms of TNFα and inhibit binding of TNFα with its receptors. Infliximab products do not neutralize TNFβ (lymphotoxin-α), a related cytokine that utilizes the same receptors as TNFα. Biological activities attributed to TNFα include: induction of pro-inflammatory cytokines such as interleukins (IL) 1 and 6, enhancement of leukocyte migration by increasing endothelial layer permeability and expression of adhesion molecules by endothelial cells and leukocytes, activation of neutrophil and eosinophil functional activity, induction of acute phase reactants and other liver proteins, as well as tissue degrading enzymes produced by synoviocytes and/or chondrocytes. Cells expressing transmembrane TNFα bound by infliximab products can be lysed in vitro or in vivo. Infliximab products inhibit the functional activity of TNFα in a wide variety of in vitro bioassays utilizing human fibroblasts, endothelial cells, neutrophils, B and T-lymphocytes and epithelial cells. The relationship of these biological response markers to the mechanism(s) by which infliximab products exert their clinical effects is unknown. Anti-TNFα antibodies reduce disease activity in the cotton-top tamarin colitis model, and decrease synovitis and joint erosions in a murine model of collagen-induced arthritis. Infliximab products prevent disease in transgenic mice that develop polyarthritis as a result of constitutive expression of human TNFα, and when administered after disease onset, allow eroded joints to heal.

12.2 Pharmacodynamics

Elevated concentrations of TNFα have been found in involved tissues and fluids of patients with RA, CD, UC, AS, PsA, and Ps. In RA, treatment with infliximab products reduced infiltration of inflammatory cells into inflamed areas of the joint as well as expression of molecules mediating cellular adhesion [E-selectin, intercellular adhesion molecule-1 (ICAM-1) and vascular cell adhesion molecule-1 (VCAM-1)], chemoattraction [IL-8 and monocyte chemotactic protein (MCP-1)] and tissue degradation [matrix metalloproteinase (MMP) 1 and 3]. In CD, treatment with infliximab products reduced infiltration of inflammatory cells and TNFα production in inflamed areas of the intestine, and reduced the proportion of mononuclear cells from the lamina propria able to express TNFα and interferon. After treatment with infliximab products, patients with RA or CD exhibited decreased levels of serum IL-6 and C-reactive protein (CRP) compared to baseline. Peripheral blood lymphocytes from infliximab product-treated patients showed no significant decrease in number or in proliferative responses to in vitro mitogenic stimulation when compared to cells from untreated patients. In PsA, treatment with infliximab products resulted in a reduction in the number of T-cells and blood vessels in the synovium and psoriatic skin lesions as well as a reduction of macrophages in the synovium. In Ps, treatment with infliximab products may reduce the epidermal thickness and infiltration of inflammatory cells. The relationship between these pharmacodynamic activities and the mechanism(s) by which infliximab products exert their clinical effects is unknown.

12.3 Pharmacokinetics

In adults, single intravenous (IV) infusions of 3 mg/kg to 20 mg/kg (two times the maximum recommended dose for any indication) of infliximab showed a linear relationship between the dose administered and the maximum serum concentration. The volume of distribution at steady state was independent of dose and indicated that infliximab was distributed primarily within the vascular compartment. Pharmacokinetic results for single doses of 3 mg/kg to 10 mg/kg in RA, 5 mg/kg in CD, and 3 mg/kg to 5 mg/kg in Ps indicate that the median terminal half-life of infliximab is 7.7 to 9.5 days.

Following an initial dose of infliximab, repeated infusions at 2 and 6 weeks resulted in predictable concentration-time profiles following each treatment. No systemic accumulation of infliximab occurred upon continued repeated treatment with 3 mg/kg or 10 mg/kg at 4- or 8-week intervals. Development of antibodies to infliximab increased infliximab clearance. At 8 weeks after a maintenance dose of 3 to 10 mg/kg of infliximab, median infliximab serum concentrations ranged from approximately 0.5 to 6 mcg/mL; however, infliximab concentrations were not detectable (<0.1 mcg/mL) in patients who became positive for antibodies to infliximab. No major differences in clearance or volume of distribution were observed in patient subgroups defined by age, weight, or gender. It is not known if there are differences in clearance or volume of distribution in patients with marked impairment of hepatic or renal function.

Infliximab pharmacokinetic characteristics (including peak and trough concentrations and terminal half-life) were similar in pediatric (aged 6 to 17 years) and adult patients with CD or UC following the administration of 5 mg/kg of infliximab.

13 NONCLINICAL TOXICOLOGY

13.1 Carcinogenesis, Mutagenesis, Impairment of Fertility

A 6-month study in CD-1 mice was conducted to assess the tumorigenic potential of cV1q anti- mouse TNFα, an analogous antibody. No evidence of tumorigenicity was observed in mice that received intravenous doses of 10 mg/kg or 40 mg/kg cV1q given weekly. The relevance of this study for human risk is unknown. No impairment of fertility or reproductive performance indices were observed in male or female mice that received cV1q, an analogous mouse antibody, at intravenous doses up to 40 mg/kg given weekly.

14 CLINICAL STUDIES

14.1 Adult Crohn's Disease

Active Crohn's Disease in Adults

The safety and efficacy of single and multiple doses of infliximab were assessed in 2 randomized, double-blind, placebo-controlled clinical studies in 653 adult patients with moderate to severely active CD [Crohn's Disease Activity Index (CDAI) ≥ 220 and ≤ 400] with an inadequate response to prior conventional therapies. Concomitant stable doses of aminosalicylates, corticosteroids and/or immunomodulatory agents were permitted and 92% of patients continued to receive at least one of these medications.

In the single-dose trial of 108 adult patients, 16% (4/25) of placebo patients achieved a clinical response (decrease in CDAI ≥ 70 points) at Week 4 vs. 81% (22/27) of patients receiving 5 mg/kg infliximab (p < 0.001, two-sided, Fisher's Exact test). Additionally, 4% (1/25) of placebo patients and 48% (13/27) of patients receiving 5 mg/kg infliximab achieved clinical remission (CDAI < 150) at Week 4.

In a multidose trial (ACCENT I [Study Crohn's I]), 545 adult patients received 5 mg/kg at Week 0 and were then randomized to one of three treatment groups; the placebo maintenance group received placebo at Weeks 2 and 6, and then every 8 weeks; the 5 mg/kg maintenance group received 5 mg/kg at Weeks 2 and 6, and then every 8 weeks; and the 10 mg/kg maintenance group received 5 mg/kg at Weeks 2 and 6, and then 10 mg/kg every 8 weeks. Patients in response at Week 2 were randomized and analyzed separately from those not in response at Week 2. Corticosteroid taper was permitted after Week 6.

At Week 2, 57% (311/545) of patients were in clinical response. At Week 30, a significantly greater proportion of these patients in the 5 mg/kg and 10 mg/kg maintenance groups achieved clinical remission compared to patients in the placebo maintenance group (Table 3). Additionally, a significantly greater proportion of patients in the 5 mg/kg and 10 mg/kg infliximab maintenance groups were in clinical remission and were able to discontinue corticosteroid use compared to patients in the placebo maintenance group at Week 54 (Table 3).

Table 3 Clinical Remission and Steroid Withdrawal in Adult Patients with CD (Study Crohn's I)
 | Single 5-mg/kg Dose [Infliximab at Week 0] | Three-Dose Induction [Infliximab 5 mg/kg administered at Weeks 0, 2 and 6]
 | Placebo Maintenance | Infliximab Maintenance q 8 wks
 |  | 5 mg/kg | 10 mg/kg
Week 30 | 25/102 | 41/104 | 48/105
Clinical remission | 25% | 39% | 46%
P-value [P-values represent pairwise comparisons to placebo] |  | 0.022 | 0.001
Week 54 | 6/54 | 14/56 | 18/53
Patients in remission able to discontinue corticosteroid use [Of those receiving corticosteroids at baseline] | 11% | 25% | 34%
P-value |  | 0.059 | 0.005

Patients in the infliximab maintenance groups (5 mg/kg and 10 mg/kg) had a longer time to loss of response than patients in the placebo maintenance group (Figure 1). At Weeks 30 and 54, significant improvement from baseline was seen among the 5 mg/kg and 10 mg/kg infliximab-treated groups compared to the placebo group in the disease-specific inflammatory bowel disease questionnaire (IBDQ), particularly the bowel and systemic components, and in the physical component summary score of the general health-related quality of life questionnaire SF-36.

Figure 1 Kaplan-Meier Estimate of the Proportion of Adults with CD Who Had Not Lost Response Through Week 54 (Study Crohn's I)

In a subset of 78 patients who had mucosal ulceration at baseline and who participated in an endoscopic substudy, 13 of 43 patients in the infliximab maintenance group had endoscopic evidence of mucosal healing compared to 1 of 28 patients in the placebo group at Week 10. Of the infliximab-treated patients showing mucosal healing at Week 10, 9 of 12 patients also showed mucosal healing at Week 54.

Patients who achieved a response and subsequently lost response were eligible to receive infliximab on an episodic basis at a dose that was 5 mg/kg higher than the dose to which they were randomized. The majority of such patients responded to the higher dose. Among patients who were not in response at Week 2, 59% (92/157) of infliximab maintenance patients responded by Week 14 compared to 51% (39/77) of placebo maintenance patients. Among patients who did not respond by Week 14, additional therapy did not result in significantly more responses [see Dosage and Administration (2)].

Fistulizing Crohn's Disease in Adults

The safety and efficacy of infliximab were assessed in 2 randomized, double-blind, placebo-controlled studies in adult patients with fistulizing CD with fistula(s) that were of at least 3 months duration. Concurrent use of stable doses of corticosteroids, 5-aminosalicylates, antibiotics, MTX, 6-mercaptopurine (6-MP) and/or azathioprine (AZA) was permitted.

In the first trial, 94 adult patients received 3 doses of either placebo or infliximab at Weeks 0, 2 and 6. Fistula response (≥ 50% reduction in number of enterocutaneous fistulas draining upon gentle compression on at least 2 consecutive visits without an increase in medication or surgery for CD) was seen in 68% (21/31) of patients in the 5 mg/kg infliximab group (P = 0.002) and 56% (18/32) of patients in the 10 mg/kg infliximab group (P = 0.021) vs. 26% (8/31) of patients in the placebo arm. The median time to onset of response and median duration of response in infliximab-treated patients was 2 and 12 weeks, respectively. Closure of all fistulas was achieved in 52% of infliximab-treated patients compared with 13% of placebo-treated patients (P < 0.001).

In the second trial (ACCENT II [Study Crohn's II]), adult patients who were enrolled had to have at least 1 draining enterocutaneous (perianal, abdominal) fistula. All patients received 5 mg/kg infliximab at Weeks 0, 2 and 6. Patients were randomized to placebo or 5 mg/kg infliximab maintenance at Week 14. Patients received maintenance doses at Week 14 and then every 8 weeks through Week 46. Patients who were in fistula response (fistula response was defined the same as in the first trial) at both Weeks 10 and 14 were randomized separately from those not in response. The primary endpoint was time from randomization to loss of response among those patients who were in fistula response.

Among the randomized patients (273 of the 296 initially enrolled), 87% had perianal fistulas and 14% had abdominal fistulas. Eight percent also had rectovaginal fistulas. Greater than 90% of the patients had received previous immunosuppressive and antibiotic therapy.

At Week 14, 65% (177/273) of patients were in fistula response. Patients randomized to infliximab maintenance had a longer time to loss of fistula response compared to the placebo maintenance group (Figure 2). At Week 54, 38% (33/87) of infliximab-treated patients had no draining fistulas compared with 22% (20/90) of placebo-treated patients (P=0.02). Compared to placebo maintenance, patients on infliximab maintenance had a trend toward fewer hospitalizations.

Figure 2 Life Table Estimates of the Proportion of Adult CD Patients Who Had Not Lost Fistula Response Through Week 54 (Study Crohn's II)

Patients who achieved a fistula response and subsequently lost response were eligible to receive infliximab maintenance therapy at a dose that was 5 mg/kg higher than the dose to which they were randomized. Of the placebo maintenance patients, 66% (25/38) responded to 5 mg/kg infliximab, and 57% (12/21) of infliximab maintenance patients responded to 10 mg/kg.

Patients who had not achieved a response by Week 14 were unlikely to respond to additional doses of infliximab.

Similar proportions of patients in either group developed new fistulas (17% overall) and similar numbers developed abscesses (15% overall).

14.2 Pediatric Crohn's Disease

The safety and efficacy of infliximab were assessed in a randomized, open-label study (Study Peds Crohn's) in 112 pediatric patients aged 6 to 17 years old with moderately to severely active CD and an inadequate response to conventional therapies. The median age was 13 years and the median Pediatric Crohn's Disease Activity Index (PCDAI) was 40 (on a scale of 0 to 100). All patients were required to be on a stable dose of 6-MP, AZA, or MTX; 35% were also receiving corticosteroids at baseline.

All patients received induction dosing of 5 mg/kg infliximab at Weeks 0, 2, and 6. At Week 10, 103 patients were randomized to a maintenance regimen of 5 mg/kg infliximab given either every 8 weeks or every 12 weeks.

At Week 10, 88% of patients were in clinical response (defined as a decrease from baseline in the PCDAI score of ≥ 15 points and total PCDAI score of ≤ 30 points), and 59% were in clinical remission (defined as PCDAI score of ≤ 10 points).

The proportion of pediatric patients achieving clinical response at Week 10 compared favorably with the proportion of adults achieving a clinical response in Study Crohn's I. The study definition of clinical response in Study Peds Crohn's was based on the PCDAI score, whereas the CDAI score was used in the adult Study Crohn's I.

At both Week 30 and Week 54, the proportion of patients in clinical response was greater in the every 8-week treatment group than in the every 12-week treatment group (73% vs. 47% at Week 30, and 64% vs. 33% at Week 54). At both Week 30 and Week 54, the proportion of patients in clinical remission was also greater in the every 8-week treatment group than in the every 12 week treatment group (60% vs. 35% at Week 30, and 56% vs. 24% at Week 54), (Table 4).

For patients in Study Peds Crohn's receiving corticosteroids at baseline, the proportion of patients able to discontinue corticosteroids while in remission at Week 30 was 46% for the every 8-week maintenance group and 33% for the every 12-week maintenance group. At Week 54, the proportion of patients able to discontinue corticosteroids while in remission was 46% for the every 8-week maintenance group and 17% for the every 12-week maintenance group.

Table 4 Response and Remission in Study Peds Crohn's
 | 5 mg/kg infliximab
 | Every 8 Week | Every 12 Week
 | Treatment Group | Treatment Group
Patients randomized | 52 | 51
Clinical Response [Defined as a decrease from baseline in the PCDAI score of ≥ 15 points and total score of ≤ 30 points.]
Week 30 | 73% [P-value < 0.01] | 47%
Week 54 | 64% | 33%
Clinical Remission [Defined as a PCDAI score of ≤ 10 points.]
Week 30 | 60% [P-value < 0.05] | 35%
Week 54 | 56% | 24%

14.3 Adult Ulcerative Colitis

The safety and efficacy of infliximab were assessed in 2 randomized, double-blind, placebo-controlled clinical studies in 728 adult patients with moderately to severely active UC (Mayo score 6 to 12 [of possible range 0 to 12], Endoscopy subscore ≥ 2) with an inadequate response to conventional oral therapies (Studies UC I and UC II). Concomitant treatment with stable doses of aminosalicylates, corticosteroids and/or immunomodulatory agents was permitted. Corticosteroid taper was permitted after Week 8. Patients were randomized at week 0 to receive either placebo, 5 mg/kg infliximab or 10 mg/kg infliximab at Weeks 0, 2, 6, and every 8 weeks thereafter through Week 46 in Study UC I, and at Weeks 0, 2, 6, and every 8 weeks thereafter through Week 22 in Study UC II. In Study UC II, patients were allowed to continue blinded therapy to Week 46 at the investigator's discretion.

Adult patients in Study UC I had failed to respond or were intolerant to oral corticosteroids, 6-MP, or AZA. Adult patients in Study UC II had failed to respond or were intolerant to the above treatments and/or aminosalicylates. Similar proportions of patients in Studies UC I and UC II were receiving corticosteroids (61% and 51%, respectively), 6-MP/AZA (49% and 43%) and aminosalicylates (70% and 75%) at baseline. More patients in Study UC II than UC I were taking solely aminosalicylates for UC (26% vs. 11%, respectively). Clinical response was defined as a decrease from baseline in the Mayo score by ≥ 30% and ≥ 3 points, accompanied by a decrease in the rectal bleeding subscore of ≥ 1 or a rectal bleeding subscore of 0 or 1.

Clinical Response, Clinical Remission, and Mucosal Healing

In both Study UC I and Study UC II, greater percentages of patients in both infliximab groups achieved clinical response, clinical remission and mucosal healing than in the placebo group. Each of these effects was maintained through the end of each trial (Week 54 in Study UC I, and Week 30 in Study UC II). In addition, a greater proportion of patients in infliximab groups demonstrated sustained response and sustained remission than in the placebo groups (Table 5).

Of patients on corticosteroids at baseline, greater proportions of adult patients in the infliximab treatment groups were in clinical remission and able to discontinue corticosteroids at Week 30 compared with the patients in the placebo treatment groups (22% in infliximab treatment groups vs. 10% in placebo group in Study UC I; 23% in infliximab treatment groups vs. 3% in placebo group in Study UC II). In Study UC I, this effect was maintained through Week 54 (21% in infliximab treatment groups vs. 9% in placebo group). The infliximab-associated response was generally similar in the 5 mg/kg and 10 mg/kg dose groups.

Table 5 Response, Remission and Mucosal Healing in Adult UC Studies (Studies UC I and UC II)
 | Study UC I |  |  |  | Study UC II
 | Placebo | 5 mg/kg infliximab | 10 mg/kg infliximab |  | Placebo | 5 mg/kg infliximab | 10 mg/kg infliximab
Patients randomized | 121 | 121 | 122 |  | 123 | 121 | 120
Clinical Response [Defined as a decrease from baseline in the Mayo score by ≥ 30% and ≥ 3 points, accompanied by a decrease in the rectal bleeding subscore of ≥ 1 or a rectal bleeding subscore of 0 or 1. (The Mayo score consists of the sum of four subscores: stool frequency, rectal bleeding, physician's global assessment and endoscopy findings).] , [Patients who had a prohibited change in medication, had an ostomy or colectomy, or discontinued study infusions due to lack of efficacy are considered to not be in clinical response, clinical remission or mucosal healing from the time of the event onward.]
Week 8 | 37% | 69% [P < 0.001,] | 62% |  | 29% | 65% | 69%
Week 30 | 30% | 52% | 51% [P < 0.01] |  | 26% | 47% | 60%
Week 54 | 20% | 45% | 44% |  | NA | NA | NA
Sustained Response
(Clinical response at both Week 8 and 30) | 23% | 49% | 46% |  | 15% | 41% | 53%
(Clinical response at Week 8, 30, and 54) | 14% | 39% | 37% |  | NA | NA | NA
Clinical Remission [Defined as a Mayo score ≤ 2 points, no individual subscore >1.] ,
Week 8 | 15% | 39% | 32% |  | 6% | 34% | 28%
Week 30 | 16% | 34% | 37% |  | 11% | 26% | 36%
Week 54 | 17% | 35% | 34% |  | NA | NA | NA
Sustained Remission
(Clinical remission at both Week 8 and 30) | 8% | 23% | 26% |  | 2% | 15% | 23%
(Clinical remission at Week 8, 30 and 54) | 7% | 20% | 20% |  | NA | NA | NA
Mucosal Healing [Defined as a 0 or 1 on the endoscopy subscore of the Mayo score.] ,
Week 8 | 34% | 62% | 59% |  | 31% | 60% | 62%
Week 30 | 25% | 50% | 49% |  | 30% | 46% | 57%
Week 54 | 18% | 45% | 47% |  | NA | NA | NA

The improvement with infliximab was consistent across all Mayo subscores through Week 54 (Study UC I shown in Table 6; Study UC II through Week 30 was similar).

Table 6 Proportion of Adult UC Patients in Study UC I with Mayo Subscores Indicating Inactive or Mild Disease Through Week 54
 | Study UC I
 |  | Infliximab
 | Placebo | 5 mg/kg | 10 mg/kg
 | (n = 121) | (n = 121) | (n = 122)
Stool frequency
Baseline | 17% | 17% | 10%
Week 8 | 35% | 60% | 58%
Week 30 | 35% | 51% | 53%
Week 54 | 31% | 52% | 51%
Rectal bleeding
Baseline | 54% | 40% | 48%
Week 8 | 74% | 86% | 80%
Week 30 | 65% | 74% | 71%
Week 54 | 62% | 69% | 67%
Physician's Global Assessment
Baseline | 4% | 6% | 3%
Week 8 | 44% | 74% | 64%
Week 30 | 36% | 57% | 55%
Week 54 | 26% | 53% | 53%
Endoscopy findings
Baseline | 0% | 0% | 0%
Week 8 | 34% | 62% | 59%
Week 30 | 26% | 51% | 52%
Week 54 | 21% | 50% | 51%

14.4 Pediatric Ulcerative Colitis

The safety and effectiveness of infliximab products for reducing signs and symptoms and inducing and maintaining clinical remission in pediatric patients aged 6 years and older with moderately to severely active UC who have had an inadequate response to conventional therapy are supported by evidence from adequate and well-controlled studies of infliximab in adults. Additional safety and pharmacokinetic data were collected in an open-label pediatric UC trial in 60 pediatric patients aged 6 through 17 years (median age 14.5 years) with moderately to severely active UC (Mayo score of 6 to 12; Endoscopic subscore ≥ 2) and an inadequate response to conventional therapies. At baseline, the median Mayo score was 8, 53% of patients were receiving immunomodulator therapy (6-MP/AZA/MTX), and 62% of patients were receiving corticosteroids (median dose 0.5 mg/kg/day in prednisone equivalents). Discontinuation of immunomodulators and corticosteroid taper were permitted after Week 0.

All patients received induction dosing of 5 mg/kg infliximab at Weeks 0, 2, and 6. Patients who did not respond to infliximab at Week 8 received no further infliximab and returned for safety follow-up. At Week 8, 45 patients were randomized to a maintenance regimen of 5 mg/kg infliximab given either every 8 weeks through Week 46 or every 12 weeks through Week 42. Patients were allowed to change to a higher dose and/or more frequent administration schedule if they experienced loss of response.

Clinical response at Week 8 was defined as a decrease from baseline in the Mayo score by ≥ 30% and ≥ 3 points, including a decrease in the rectal bleeding subscore by ≥ 1 points or achievement of a rectal bleeding subscore of 0 or 1.

Clinical remission at Week 8 was measured by the Mayo score, defined as a Mayo score of ≤ 2 points with no individual subscore >1. Clinical remission was also assessed at Week 8 and Week 54 using the Pediatric Ulcerative Colitis Activity Index (PUCAI)^1 score and was defined by a PUCAI score of <10 points.

Endoscopies were performed at baseline and at Week 8. A Mayo endoscopy subscore of 0 indicated normal or inactive disease and a subscore of 1 indicated mild disease (erythema, decreased vascular pattern, or mild friability).

Of the 60 patients treated, 44 were in clinical response at Week 8. Of 32 patients taking concomitant immunomodulators at baseline, 23 achieved clinical response at Week 8, compared to 21 of 28 of those not taking concomitant immunomodulators at baseline. At Week 8, 24 of 60 patients were in clinical remission as measured by the Mayo score and 17 of 51 patients were in remission as measured by the PUCAI score.

At Week 54, 8 of 21 patients in the every 8-week maintenance group and 4 of 22 patients in the every 12-week maintenance group achieved remission as measured by the PUCAI score.

During maintenance phase, 23 of 45 randomized patients (9 in the every 8-week group and 14 in the every 12-week group) required an increase in their dose and/or increase in frequency of infliximab administration due to loss of response. Nine of the 23 patients who required a change in dose had achieved remission at Week 54. Seven of those patients received the 10 mg/kg every 8-week dosing.

14.5 Rheumatoid Arthritis

The safety and efficacy of infliximab in adult patients with RA were assessed in 2 multicenter, randomized, double-blind, pivotal trials: ATTRACT (Study RA I) and ASPIRE (Study RA II). Concurrent use of stable doses of folic acid, oral corticosteroids (≤ 10 mg/day) and/or non-steroidal anti-inflammatory drugs (NSAIDs) was permitted.

Study RA I was a placebo-controlled study of 428 patients with active RA despite treatment with MTX. Patients enrolled had a median age of 54 years, median disease duration of 8.4 years, median swollen and tender joint count of 20 and 31 respectively, and were on a median dose of 15 mg/wk of MTX. Patients received either placebo+MTX or one of 4 doses/schedules of infliximab+MTX: 3 mg/kg or 10 mg/kg of infliximab by IV infusion at Weeks 0, 2 and 6 followed by additional infusions every 4 or 8 weeks in combination with MTX.

Study RA II was a placebo-controlled study of 3 active treatment arms in 1004 MTX naive patients of 3 or fewer years' duration active RA. Patients enrolled had a median age of 51 years with a median disease duration of 0.6 years, median swollen and tender joint count of 19 and 31, respectively, and >80% of patients had baseline joint erosions. At randomization, all patients received MTX (optimized to 20 mg/wk by Week 8) and either placebo, 3 mg/kg or 6 mg/kg infliximab at Weeks 0, 2, and 6 and every 8 weeks thereafter.

Data on use of infliximab products without concurrent MTX are limited [see Adverse Reactions (6.1)].

Clinical Response

In Study RA I, all doses/schedules of infliximab+MTX resulted in improvement in signs and symptoms as measured by the American College of Rheumatology response criteria (ACR 20) with a higher percentage of patients achieving an ACR 20, 50 and 70 compared to placebo+MTX (Table 7). This improvement was observed at Week 2 and maintained through Week 102. Greater effects on each component of the ACR 20 were observed in all patients treated with infliximab+MTX compared to placebo+MTX (Table 8). More patients treated with infliximab reached a major clinical response than placebo-treated patients (Table 7).

In Study RA II, after 54 weeks of treatment, both doses of infliximab+MTX resulted in statistically significantly greater response in signs and symptoms compared to MTX alone as measured by the proportion of patients achieving ACR 20, 50 and 70 responses (Table 7). More patients treated with infliximab reached a major clinical response than placebo-treated patients (Table 7).

Table 7 ACR Response (percent of patients) in Adult RA Patients (Studies RA I and RA II)
 | Study RA I |  |  |  |  | Study RA II
 |  | Infliximab+MTX |  |  |  |  | Infliximab+MTX
 |  | 3 mg/kg |  | 10 mg/kg |  |  | 3 mg/kg | 6 mg/kg
Response | Placebo+MTX | q8 wks | q4 wks | q8 wks | q4 wks | Placebo+MTX | q8 wks | q8 wks
 | (n = 88) | (n = 86) | (n = 86) | (n = 87) | (n = 81) | (n = 274) | (n = 351) | (n = 355)
ACR20
Week 30 | 20% | 50% [P ≤ 0.001] | 50% | 52% | 58% | N/A | N/A | N/A
Week 54 | 17% | 42% | 48% | 59% | 59% | 54% | 62% [P < 0.05] | 66%
ACR50
Week 30 | 5% | 27% | 29% | 31% | 26% | N/A | N/A | N/A
Week 54 | 9% | 21% | 34% | 40% | 38% | 32% | 46% | 50%
ACR70
Week 30 | 0% | 8% [P < 0.01] | 11% | 18% | 11% | N/A | N/A | N/A
Week 54 | 2% | 11% | 18% | 26% | 19% | 21% | 33% | 37%
Major clinical response [A major clinical response was defined as a 70% ACR response for 6 consecutive months (consecutive visits spanning at least 26 weeks) through Week 102 for Study RA I and Week 54 for Study RA II.] | 0% | 7% | 8% | 15% | 6% | 8% | 12% | 17%

Table 8 Components of ACR 20 at Baseline and 54 Weeks (Study RA I)
 | Placebo+MTX |  | Infliximab+MTX [All doses/schedules of infliximab+MTX]
 | (n = 88) |  | (n = 340)
Parameter (medians) | Baseline | Week 54 | Baseline | Week 54
No. of Tender Joints | 24 | 16 | 32 | 8
No. of Swollen Joints | 19 | 13 | 20 | 7
Pain [Visual Analog Scale (0=best, 10=worst)] | 6.7 | 6.1 | 6.8 | 3.3
Physician's Global Assessment | 6.5 | 5.2 | 6.2 | 2.1
Patient's Global Assessment | 6.2 | 6.2 | 6.3 | 3.2
Disability Index (HAQ-DI) [Health Assessment Questionnaire, measurement of 8 categories: dressing and grooming, arising, eating, walking, hygiene, reach, grip, and activities (0=best, 3=worst)] | 1.8 | 1.5 | 1.8 | 1.3
CRP (mg/dL) | 3.0 | 2.3 | 2.4 | 0.6

Radiographic Response

Structural damage in both hands and feet was assessed radiographically at Week 54 by the change from baseline in the van der Heijde-modified Sharp (vdH-S) score, a composite score of structural damage that measures the number and size of joint erosions and the degree of joint space narrowing in hands/wrists and feet.

In Study RA I, approximately 80% of patients had paired X-ray data at 54 weeks and approximately 70% at 102 weeks. The inhibition of progression of structural damage was observed at 54 weeks (Table 9) and maintained through 102 weeks.

In Study RA II, >90% of patients had at least 2 evaluable X-rays. Inhibition of progression of structural damage was observed at Weeks 30 and 54 (Table 9) in the infliximab+MTX groups compared to MTX alone. Patients treated with infliximab+MTX demonstrated less progression of structural damage compared to MTX alone, whether baseline acute-phase reactants (ESR and CRP) were normal or elevated: patients with elevated baseline acute-phase reactants treated with MTX alone demonstrated a mean progression in vdH-S score of 4.2 units compared to patients treated with infliximab+MTX who demonstrated 0.5 units of progression; patients with normal baseline acute phase reactants treated with MTX alone demonstrated a mean progression in vdH-S score of 1.8 units compared to infliximab+MTX who demonstrated 0.2 units of progression. Of patients receiving infliximab+MTX, 59% had no progression (vdH-S score ≤ 0 unit) of structural damage compared to 45% of patients receiving MTX alone. In a subset of patients who began the study without erosions, infliximab+MTX maintained an erosion-free state at 1 year in a greater proportion of patients than MTX alone, 79% (77/98) vs. 58% (23/40), respectively (P<0.01). Fewer patients in the infliximab+MTX groups (47%) developed erosions in uninvolved joints compared to MTX alone (59%).

Table 9 Radiographic Change from Baseline to Week 54 in Adult RA Patients (Studies RA I and RA II)
 | Study RA I |  |  |  | Study RA II
 |  | Infliximab+MTX |  |  |  | Infliximab+MTX
 | Placebo + MTX (n = 64) | 3 mg/kg q8 wks (n = 71) | 10 mg/kg q8 wks (n = 77) |  | Placebo + MTX (n = 282) | 3 mg/kg q8 wks (n = 359) | 6 mg/kg q8 wks (n = 363)
Total Score
Baseline
Mean | 79 | 78 | 65 |  | 11.3 | 11.6 | 11.2
Median | 55 | 57 | 56 |  | 5.1 | 5.2 | 5.3
Change from baseline
Mean | 6.9 | 1.3 [P < 0.001 for each outcome against placebo.] | 0.2 |  | 3.7 | 0.4 | 0.5
Median | 4.0 | 0.5 | 0.5 |  | 0.4 | 0.0 | 0.0
Erosion Score
Baseline
Mean | 44 | 44 | 33 |  | 8.3 | 8.8 | 8.3
Median | 25 | 29 | 22 |  | 3.0 | 3.8 | 3.8
Change from baseline
Mean | 4.1 | 0.2 | 0.2 |  | 3.0 | 0.3 | 0.1
Median | 2.0 | 0.0 | 0.5 |  | 0.3 | 0.0 | 0.0
JSN Score
Baseline
Mean | 36 | 34 | 31 |  | 3.0 | 2.9 | 2.9
Median | 26 | 29 | 24 |  | 1.0 | 1.0 | 1.0
Change from baseline
Mean | 2.9 | 1.1 | 0.0 |  | 0.6 | 0.1 | 0.2
Median | 1.5 | 0.0 | 0.0 |  | 0.0 | 0.0 | 0.0

Physical Function Response

Physical function and disability were assessed using the Health Assessment Questionnaire (HAQ-DI) and the general health-related quality of life questionnaire SF-36.

In Study RA I, all doses/schedules of infliximab+MTX showed significantly greater improvement from baseline in HAQ-DI and SF-36 physical component summary score averaged over time through Week 54 compared to placebo+MTX, and no worsening in the SF-36 mental component summary score. The median (interquartile range) improvement from baseline to Week 54 in HAQ-DI was 0.1 (-0.1, 0.5) for the placebo+MTX group and 0.4 (0.1, 0.9) for infliximab+MTX (p<0.001). Both HAQ-DI and SF-36 effects were maintained through Week 102. Approximately 80% of patients in all doses/schedules of infliximab+MTX remained in the trial through 102 weeks.

In Study RA II, both infliximab treatment groups showed greater improvement in HAQ-DI from baseline averaged over time through Week 54 compared to MTX alone; 0.7 for infliximab+MTX vs. 0.6 for MTX alone (P ≤ 0.001). No worsening in the SF-36 mental component summary score was observed.

14.6 Ankylosing Spondylitis

The safety and efficacy of infliximab were assessed in a randomized, multicenter, double-blind, placebo-controlled study in 279 adult patients with active AS. Patients were between 18 and 74 years of age, and had AS as defined by the modified New York criteria for Ankylosing Spondylitis. Patients were to have had active disease as evidenced by both a Bath Ankylosing Spondylitis Disease Activity Index (BASDAI) score >4 (possible range 0-10) and spinal pain >4 (on a Visual Analog Scale [VAS] of 0-10). Patients with complete ankylosis of the spine were excluded from study participation, and the use of Disease Modifying Anti-Rheumatic Drugs (DMARDs) and systemic corticosteroids were prohibited. Doses of infliximab 5 mg/kg or placebo were administered intravenously at Weeks 0, 2, 6, 12 and 18.

At 24 weeks, improvement in the signs and symptoms of AS, as measured by the proportion of patients achieving a 20% improvement in ASAS response criteria (ASAS 20), was seen in 60% of patients in the infliximab-treated group vs. 18% of patients in the placebo group (p<0.001). Improvement was observed at Week 2 and maintained through Week 24 (Figure 3 and Table 10).

Figure 3 Proportion of Adult AS Patients Who Achieved a ASAS 20 Response

At 24 weeks, the proportions of patients achieving a 50% and a 70% improvement in the signs and symptoms of AS, as measured by ASAS response criteria (ASAS 50 and ASAS 70, respectively), were 44% and 28%, respectively, for patients receiving infliximab, compared to 9% and 4%, respectively, for patients receiving placebo (P < 0.001, infliximab vs. placebo). A low level of disease activity (defined as a value < 20 [on a scale of 0-100 mm] in each of the 4 ASAS response parameters) was achieved in 22% of infliximab-treated patients vs. 1% in placebo-treated patients (P < 0.001).

Table 10 Components of AS Disease Activity
 | Placebo (n = 78) |  | Infliximab 5 mg/kg (n = 201)
 | Baseline | 24 Weeks | Baseline | 24 Weeks | P-value
ASAS 20 response Criteria (Mean)
Patient Global Assessment [Measured on a VAS with 0 = "none" and 10 = "severe"] | 6.6 | 6.0 | 6.8 | 3.8 | < 0.001
Spinal pain | 7.3 | 6.5 | 7.6 | 4.0 | < 0.001
BASFI [Bath Ankylosing Spondylitis Functional Index (BASFI), average of 10 questions] | 5.8 | 5.6 | 5.7 | 3.6 | < 0.001
Inflammation [Inflammation, average of last 2 questions on the 6-question BASDAI] | 6.9 | 5.8 | 6.9 | 3.4 | < 0.001
Acute Phase Reactants
Median CRP [CRP normal range 0-1.0 mg/dL] (mg/dL) | 1.7 | 1.5 | 1.5 | 0.4 | < 0.001
Spinal Mobility (cm, Mean)
Modified Schober's test [Spinal mobility normal values: modified Schober's test: > 4 cm; chest expansion: > 6 cm; tragus to wall: < 15 cm; lateral spinal flexion: > 10 cm] | 4.0 | 5.0 | 4.3 | 4.4 | 0.75
Chest expansion | 3.6 | 3.7 | 3.3 | 3.9 | 0.04
Tragus to wall | 17.3 | 17.4 | 16.9 | 15.7 | 0.02
Lateral spinal flexion | 10.6 | 11.0 | 11.4 | 12.9 | 0.03

The median improvement from baseline in the general health-related quality-of-life questionnaire SF-36 physical component summary score at Week 24 was 10.2 for the infliximab group vs. 0.8 for the placebo group (P < 0.001). There was no change in the SF-36 mental component summary score in either the infliximab group or the placebo group.

Results of this study were similar to those seen in a multicenter double-blind, placebo-controlled study of 70 patients with AS.

14.7 Psoriatic Arthritis

Safety and efficacy of infliximab were assessed in a multicenter, double-blind, placebo-controlled study in 200 adult patients with active PsA despite DMARD or NSAID therapy (≥ 5 swollen joints and ≥ 5 tender joints) with 1 or more of the following subtypes: arthritis involving DIP joints (n = 49), arthritis mutilans (n = 3), asymmetric peripheral arthritis (n = 40), polyarticular arthritis (n = 100), and spondylitis with peripheral arthritis (n = 8). Patients also had Ps with a qualifying target lesion ≥ 2 cm in diameter. Forty-six percent of patients continued on stable doses of methotrexate (≤ 25 mg/week). During the 24-week double-blind phase, patients received either 5 mg/kg infliximab or placebo at Weeks 0, 2, 6, 14, and 22 (100 patients in each group). At Week 16, placebo patients with < 10% improvement from baseline in both swollen and tender joint counts were switched to infliximab induction (early escape). At Week 24, all placebo-treated patients crossed over to infliximab induction. Dosing continued for all patients through Week 46.

Clinical Response

Treatment with infliximab resulted in improvement in signs and symptoms, as assessed by the ACR criteria, with 58% of infliximab-treated patients achieving ACR 20 at Week 14, compared with 11% of placebo-treated patients (P < 0.001). The response was similar regardless of concomitant use of methotrexate. Improvement was observed as early as Week 2. At 6 months, the ACR 20/50/70 responses were achieved by 54%, 41%, and 27%, respectively, of patients receiving infliximab compared to 16%, 4%, and 2%, respectively, of patients receiving placebo. Similar responses were seen in patients with each of the subtypes of PsA, although few patients were enrolled with the arthritis mutilans and spondylitis with peripheral arthritis subtypes.

Compared to placebo, treatment with infliximab resulted in improvements in the components of the ACR response criteria, as well as in dactylitis and enthesopathy (Table 11). The clinical response was maintained through Week 54. Similar ACR responses were observed in an earlier randomized, placebo-controlled study of 104 PsA patients, and the responses were maintained through 98 weeks in an open-label extension phase.

Table 11 Components of ACR 20 and Percentage of Adult PsA Patients with 1 or More Joints with Dactylitis and Percentage of Adult PsA Patients with Enthesopathy at Baseline and Week 24
 | Placebo |  | Infliximab 5 mg/kg [P<0.001 for percent change from baseline in all components of ACR 20 at Week 24, P<0.05 for % of patients with dactylitis, and P=0.004 for % of patients with enthesopathy at Week 24]
Patients Randomized | (n = 100) |  | (n = 100)
 | Baseline | Week 24 | Baseline | Week 24
Parameter (medians)
No. of Tender Joints [Scale 0-68] | 24 | 20 | 20 | 6
No. of Swollen Joints [Scale 0-66] | 12 | 9 | 12 | 3
Pain [Visual Analog Scale (0=best, 10=worst)] | 6.4 | 5.6 | 5.9 | 2.6
Physician's Global Assessment | 6.0 | 4.5 | 5.6 | 1.5
Patient's Global Assessment | 6.1 | 5.0 | 5.9 | 2.5
Disability Index (HAQ-DI) [Health Assessment Questionnaire, measurement of 8 categories: dressing and grooming, arising, eating, walking, hygiene, reach, grip, and activities (0=best, 3=worst)] | 1.1 | 1.1 | 1.1 | 0.5
CRP (mg/dL) [Normal range 0-0.6 mg/dL] | 1.2 | 0.9 | 1.0 | 0.4
% Patients with 1 or more digits with dactylitis | 41 | 33 | 40 | 15
% Patients with enthesopathy | 35 | 36 | 42 | 22

Improvement in Psoriasis Area and Severity Index (PASI) in PsA patients with baseline body surface area (BSA) ≥ 3% (n = 87 placebo, n = 83 infliximab) was achieved at Week 14, regardless of concomitant methotrexate use, with 64% of infliximab-treated patients achieving at least 75% improvement from baseline vs. 2% of placebo-treated patients; improvement was observed in some patients as early as Week 2. At 6 months, the PASI 75 and PASI 90 responses were achieved by 60% and 39%, respectively, of patients receiving infliximab compared to 1% and 0%, respectively, of patients receiving placebo. The PASI response was generally maintained through Week 54. [see Clinical Studies (14.8)].

Radiographic Response

Structural damage in both hands and feet was assessed radiographically by the change from baseline in the van der Heijde-Sharp (vdH-S) score, modified by the addition of hand DIP joints. The total modified vdH-S score is a composite score of structural damage that measures the number and size of joint erosions and the degree of joint space narrowing (JSN) in the hands and feet. At Week 24, infliximab-treated patients had less radiographic progression than placebo-treated patients (mean change of -0.70 vs. 0.82, P < 0.001). infliximab-treated patients also had less progression in their erosion scores (-0.56 vs 0.51) and JSN scores (-0.14 vs 0.31).

The patients in the infliximab group demonstrated continued inhibition of structural damage at Week 54. Most patients showed little or no change in the vdH-S score during this 12-month study (median change of 0 in both patients who initially received infliximab or placebo). More patients in the placebo group (12%) had readily apparent radiographic progression compared with the infliximab group (3%).

Physical Function

Physical function status was assessed using the HAQ Disability Index (HAQ-DI) and the SF-36 Health Survey. infliximab-treated patients demonstrated significant improvement in physical function as assessed by HAQ-DI (median percent improvement in HAQ-DI score from baseline to Week 14 and 24 of 43% for infliximab-treated patients vs 0% for placebo-treated patients).

During the placebo-controlled portion of the trial (24 weeks), 54% of infliximab-treated patients achieved a clinically meaningful improvement in HAQ-DI (≥ 0.3 unit decrease) compared to 22% of placebo-treated patients. infliximab-treated patients also demonstrated greater improvement in the SF-36 physical and mental component summary scores than placebo-treated patients. The responses were maintained for up to 2 years in an open-label extension study.

14.8 Plaque Psoriasis

The safety and efficacy of infliximab were assessed in 3 randomized, double-blind, placebo-controlled studies in patients 18 years of age and older with chronic, stable Ps involving ≥ 10% BSA, a minimum PASI score of 12, and who were candidates for systemic therapy or phototherapy. Patients with guttate, pustular, or erythrodermic psoriasis were excluded from these studies. No concomitant anti-psoriatic therapies were allowed during the study, with the exception of low-potency topical corticosteroids on the face and groin after Week 10 of study initiation.

Study I (EXPRESS) evaluated 378 patients who received placebo or infliximab at a dose of 5 mg/kg at Weeks 0, 2, and 6 (induction therapy), followed by maintenance therapy every 8 weeks. At Week 24, the placebo group crossed over to infliximab induction therapy (5 mg/kg), followed by maintenance therapy every 8 weeks. Patients originally randomized to infliximab continued to receive infliximab 5 mg/kg every 8 weeks through Week 46. Across all treatment groups, the median baseline PASI score was 21 and the baseline Static Physician Global Assessment (sPGA) score ranged from moderate (52% of patients) to marked (36%) to severe (2%). In addition, 75% of patients had a BSA > 20%. Seventy-one percent of patients previously received systemic therapy, and 82% received phototherapy.

Study II (EXPRESS II) evaluated 835 patients who received placebo or infliximab at doses of 3 mg/kg or 5 mg/kg at Weeks 0, 2, and 6 (induction therapy). At Week 14, within each infliximab dose group, patients were randomized to either scheduled (every 8 weeks) or as needed (PRN) maintenance treatment through Week 46. At Week 16, the placebo group crossed over to infliximab induction therapy (5 mg/kg), followed by maintenance therapy every 8 weeks. Across all treatment groups, the median baseline PASI score was 18, and 63% of patients had a BSA > 20%. Fifty-five percent of patients previously received systemic therapy, and 64% received a phototherapy.

Study III (SPIRIT) evaluated 249 patients who had previously received either psoralen plus ultraviolet A treatment (PUVA) or other systemic therapy for their psoriasis. These patients were randomized to receive either placebo or infliximab at doses of 3 mg/kg or 5 mg/kg at Weeks 0, 2, and 6. At Week 26, patients with a sPGA score of moderate or worse (greater than or equal to 3 on a scale of 0 to 5) received an additional dose of the randomized treatment. Across all treatment groups, the median baseline PASI score was 19, and the baseline sPGA score ranged from moderate (62% of patients) to marked (22%) to severe (3%). In addition, 75% of patients had a BSA >20%. Of the enrolled patients, 114 (46%) received the Week 26 additional dose.

In Studies I, II and III, the primary endpoint was the proportion of patients who achieved a reduction in score of at least 75% from baseline at Week 10 by the PASI (PASI 75). In Study I and Study III, another evaluated outcome included the proportion of patients who achieved a score of "cleared" or "minimal" by the sPGA. The sPGA is a 6-category scale ranging from "5 = severe" to "0 = cleared" indicating the physician's overall assessment of the psoriasis severity focusing on induration, erythema, and scaling. Treatment success, defined as "cleared" or "minimal," consisted of none or minimal elevation in plaque, up to faint red coloration in erythema, and none or minimal fine scale over < 5% of the plaque.

Study II also evaluated the proportion of patients who achieved a score of "clear" or "excellent" by the relative Physician's Global Assessment (rPGA). The rPGA is a 6-category scale ranging from "6 = worse" to "1 = clear" that was assessed relative to baseline. Overall lesions were graded with consideration to the percent of body involvement as well as overall induration, scaling, and erythema. Treatment success, defined as "clear" or "excellent," consisted of some residual pinkness or pigmentation to marked improvement (nearly normal skin texture; some erythema may be present). The results of these studies are presented in Table 12.

Table 12 Adult Psoriasis Studies I, II, and III, Percentage of Patients Who Achieved PASI 75 and Percentage Who Achieved Treatment "Success" with Physician's Global Assessment at Week 10
 | Placebo | Infliximab
 |  | 3 mg/kg | 5 mg/kg
Psoriasis Study I -patients randomized [Patients with missing data at Week 10 were considered as nonresponders.] | 77 | - | 301
PASI 75 | 2 (3%) | - | 242 (80%) [P < 0.001 compared with placebo]
sPGA | 3 (4%) | - | 242 (80%)
Psoriasis Study II -patients randomized | 208 | 313 | 314
PASI 75 | 4 (2%) | 220 (70%) | 237 (75%)
rPGA | 2 (1%) | 217 (69%) | 234 (75%)
Psoriasis Study III -patients randomized [Patients with missing data at Week 10 were imputed by last observation.] | 51 | 99 | 99
PASI 75 | 3 (6%) | 71 (72%) | 87 (88%)
sPGA | 5 (10%) | 71 (72%) | 89 (90%)

In Study I, in the subgroup of patients with more extensive Ps who had previously received phototherapy, 85% of patients on 5 mg/kg infliximab achieved a PASI 75 at Week 10 compared with 4% of patients on placebo.

In Study II, in the subgroup of patients with more extensive Ps who had previously received phototherapy, 72% and 77% of patients on 3 mg/kg and 5 mg/kg infliximab achieved a PASI 75 at Week 10 respectively compared with 1% on placebo. In Study II, among patients with more extensive Ps who had failed or were intolerant to phototherapy, 70% and 78% of patients on 3 mg/kg and 5 mg/kg infliximab achieved a PASI 75 at Week 10 respectively, compared with 2% on placebo.

Maintenance of response was studied in a subset of 292 and 297 infliximab-treated patients in the 3 mg/kg and 5 mg/kg groups; respectively, in Study II. Stratified by PASI response at Week 10 and investigational site, patients in the active treatment groups were re-randomized to either a scheduled or as needed maintenance (PRN) therapy, beginning on Week 14.

The groups that received a maintenance dose every 8 weeks appear to have a greater percentage of patients maintaining a PASI 75 through Week 50 as compared to patients who received the as-needed or PRN doses, and the best response was maintained with the 5 mg/kg every 8-week dose. These results are shown in Figure 4. At Week 46, when infliximab serum concentrations were at trough level, in the every 8-week dose group, 54% of patients in the 5 mg/kg group compared to 36% in the 3 mg/kg group achieved PASI 75. The lower percentage of PASI 75 responders in the 3 mg/kg every 8-week dose group compared to the 5 mg/kg group was associated with a lower percentage of patients with detectable trough serum infliximab levels.

This may be related in part to higher antibody rates [see Adverse Reactions (6.1)]. In addition, in a subset of patients who had achieved a response at Week 10, maintenance of response appears to be greater in patients who received infliximab every 8 weeks at the 5 mg/kg dose. Regardless of whether the maintenance doses are PRN or every 8 weeks, there is a decline in response in a subpopulation of patients in each group over time. The results of Study I through Week 50 in the 5 mg/kg every 8 weeks maintenance dose group were similar to the results from Study II.

Figure 4 Proportion of Adult Ps Patients Who Achieved ≥ 75% Improvement in PASI from Baseline through Week 50 (patients randomized at Week 14)

Efficacy and safety of infliximab treatment beyond 50 weeks have not been evaluated in patients with Ps.

15 REFERENCES

1. Turner D, Otley AR, Mack D, et al. Development, validation, and evaluation of a pediatric ulcerative colitis activity index: A prospective multicenter study. Gastroenterology. 2007;133:423–432.

16 HOW SUPPLIED/STORAGE AND HANDLING

How Supplied

Each RENFLEXIS® (infliximab-abda) for injection is supplied as one single-dose vial individually packaged in a carton (NDC 78206-162-01).

Each single-dose vial contains 100 mg of infliximab-abda as a sterile, preservative-free, white lyophilized powder for reconstitution and dilution (more than one vial may be needed for a full dose) [see Dosage and Administration (2.11)].

Storage and Handling

Store unopened RENFLEXIS® vials in a refrigerator at 2°C to 8°C (36°F to 46°F).

If needed, unopened RENFLEXIS vials may be stored at room temperatures up to a maximum of 30°C (86°F) for a single period of up to 6 months but not exceeding the original expiration date. Once removed from the refrigerator, RENFLEXIS cannot be returned to the refrigerator.

For storage conditions of the reconstituted and diluted product for administration, see Dosage and Administration (2.11).

17 PATIENT COUNSELING INFORMATION

Advise the patient or their caregiver to read the FDA-approved patient labeling (Medication Guide).

Patients or their caregivers should be advised of the potential benefits and risks of RENFLEXIS. Healthcare providers should instruct their patients or their caregivers to read the Medication Guide before starting RENFLEXIS therapy and to reread it each time they receive an infusion.

Infections

Inform patients that RENFLEXIS increases the risk for developing serious infections. Instruct patients of the importance of contacting their healthcare provider if they develop any symptoms of an infection, including tuberculosis, invasive fungal infections, and reactivation of hepatitis B virus infections [see Warnings and Precautions (5.1, 5.3)].

Malignancies

Malignancies have been reported among children, adolescents and young adults who received treatment with TNF blockers. Patients should be counseled about the risk of lymphoma and other malignancies while receiving RENFLEXIS [see Warnings and Precautions (5.2)].

Hepatotoxicity

Instruct patients to seek medical attention if they develop signs or symptoms of hepatotoxicity (e.g., jaundice) [see Warnings and Precautions (5.4)].

Heart Failure

Instruct patients to seek medical attention and consult their prescriber if they develop signs or symptoms of heart failure [see Contraindications (4) and Warnings and Precautions (5.5)].

Hematologic Reactions

Instruct patients to seek immediate medical attention if they develop signs and symptoms suggestive of blood dyscrasias or infection (e.g., persistent fever) while on RENFLEXIS [see Warnings and Precautions (5.6)].

Hypersensitivity

Advise patients to seek immediate medical attention if they experience any symptoms of serious hypersensitivity reactions [see Warnings and Precautions (5.7)].

Cardiovascular and Cerebrovascular Reactions During and After Infusion

Advise patients to seek immediate medical attention if they develop any new or worsening symptoms of cardiovascular and cerebrovascular reactions which have been reported during and within 24 hours of initiation of RENFLEXIS infusion [see Warnings and Precautions (5.8)].

Neurologic Reactions

Advise patients to seek medical attention if they develop signs or symptoms of neurologic reactions [see Warnings and Precautions (5.9)].

Live Vaccines/Therapeutic Infectious Agents

Instruct RENFLEXIS-treated patients to avoid receiving live vaccines or therapeutic infectious agents [see Warnings and Precautions (5.13)].

Manufactured by: Samsung Bioepis Co., Ltd., 76, Songdogyoyuk-ro, Yeonsu-gu, Incheon, 21987, Republic of Korea
U.S. License No. 2046

Manufactured for: Organon LLC, a subsidiary of
ORGANON & Co.,
Jersey City, NJ 07302, USA

The trademarks above are owned by their respective owners.

MEDICATION GUIDE
RENFLEXIS® (Ren-FLEK-sis)
(infliximab-abda)
for injection, for intravenous use

Read the Medication Guide that comes with RENFLEXIS before you receive the first treatment, and before each time you get a treatment of RENFLEXIS. This Medication Guide does not take the place of talking with your doctor about your medical condition or treatment.

What is the most important information I should know about RENFLEXIS?
RENFLEXIS may cause serious side effects, including:
1. Risk of infection
RENFLEXIS is a medicine that affects your immune system. RENFLEXIS can lower the ability of your immune system to fight infections. Serious infections have happened in patients receiving RENFLEXIS. These infections include tuberculosis (TB) and infections caused by viruses, fungi or bacteria that have spread throughout the body. Some patients have died from these infections.

- Your doctor should test you for TB before starting RENFLEXIS.
- Your doctor should monitor you closely for signs and symptoms of TB during treatment with RENFLEXIS.

Before starting RENFLEXIS, tell your doctor if you:

- think you have an infection. You should not start receiving RENFLEXIS if you have any kind of infection.
- are being treated for an infection.
- have signs of an infection, such as a fever, cough, flu-like symptoms.
- have any open cuts or sores on your body.
- get a lot of infections or have infections that keep coming back.
- have diabetes or an immune system problem. People with these conditions have a higher chance for infections.
- have TB, or have been in close contact with someone with TB.
- live or have lived in certain parts of the country (such as the Ohio and Mississippi River valleys) where there is an increased risk for getting certain kinds of fungal infections (histoplasmosis, coccidioidomycosis, or blastomycosis). These infections may develop or become more severe if you receive RENFLEXIS. If you do not know if you have lived in an area where histoplasmosis, coccidioidomycosis, or blastomycosis is common, ask your doctor.
- have or have had hepatitis B.
- use the medicines KINERET (anakinra), ORENCIA (abatacept), ACTEMRA (tocilizumab), or other medicines called biologics used to treat the same conditions as RENFLEXIS.

After starting RENFLEXIS, if you have an infection, any sign of an infection including a fever, cough, flu-like symptoms, or have open cuts or sores on your body, call your doctor right away. RENFLEXIS can make you more likely to get infections or make any infection that you have worse.
2. Risk of Cancer

- There have been cases of unusual cancers in children and teenage patients using tumor necrosis factor (TNF) blocker medicines, such as RENFLEXIS.
- For children and adults receiving TNF blocker medicines, including RENFLEXIS, the chances of getting lymphoma or other cancers may increase.
- Some people receiving TNF blockers, including RENFLEXIS, developed a rare type of cancer called hepatosplenic T-cell lymphoma. This type of cancer often results in death. Most of these people were male teenagers or young men. Also, most people were being treated for Crohn's disease or ulcerative colitis with a TNF blocker and another medicine called azathioprine or 6-mercaptopurine.
- People who have been treated for rheumatoid arthritis, Crohn's disease, ulcerative colitis, ankylosing spondylitis, psoriatic arthritis and plaque psoriasis for a long time may be more likely to develop lymphoma. This is especially true for people with very active disease.
- Some people treated with infliximab products, such as RENFLEXIS, have developed certain kinds of skin cancer. If any changes in the appearance of your skin or growths on your skin occur during or after your treatment with RENFLEXIS, tell your doctor.
- Patients with Chronic Obstructive Pulmonary Disease (COPD), a specific type of lung disease, may have an increased risk for getting cancer while being treated with RENFLEXIS.
- Some women being treated for rheumatoid arthritis with infliximab products have developed cervical cancer. For women receiving RENFLEXIS, including those over 60 years of age, your doctor may recommend that you continue to be regularly screened for cervical cancer.
- Tell your doctor if you have ever had any type of cancer. Discuss with your doctor any need to adjust medicines you may be taking.

See the section "What are the possible side effects of RENFLEXIS?" below for more information.

What is RENFLEXIS?
RENFLEXIS is a prescription medicine that is approved for patients with:

- Rheumatoid Arthritis - adults with moderately to severely active rheumatoid arthritis, along with the medicine methotrexate.
- Crohn's Disease - children 6 years and older and adults with Crohn's disease who have not responded well to other medicines.
- Ankylosing Spondylitis in adults
- Psoriatic Arthritis in adults
- Plaque Psoriasis - adult patients with plaque psoriasis that is chronic (does not go away), severe, extensive, and/or disabling.
- Ulcerative Colitis - children 6 years and older and adults with moderately to severely active ulcerative colitis who have not responded well to other medicines.

RENFLEXIS blocks the action of a protein in your body called tumor necrosis factor-alpha (TNF-alpha). TNF-alpha is made by your body's immune system. People with certain diseases have too much TNF-alpha that can cause the immune system to attack normal healthy parts of the body. RENFLEXIS can block the damage caused by too much TNF-alpha.
It is not known if RENFLEXIS is safe and effective in children under 6 years of age.

Who should not receive RENFLEXIS?
You should not receive RENFLEXIS if you have:

- heart failure, unless your doctor has examined you and decided that you are able to receive RENFLEXIS. Talk to your doctor about your heart failure.
- had an allergic reaction to infliximab products, or any of the ingredients in RENFLEXIS. See the end of this Medication Guide for a complete list of ingredients in RENFLEXIS.

What should I tell my doctor before starting treatment with RENFLEXIS?
Your doctor will assess your health before each treatment.
Tell your doctor about all of your medical conditions, including if you:

- have an infection (see "What is the most important information I should know about RENFLEXIS?").
- have other liver problems including liver failure.
- have heart failure or other heart conditions. If you have heart failure, it may get worse while you receive RENFLEXIS.
- have or have had any type of cancer.
- have had phototherapy (treatment with ultraviolet light or sunlight along with a medicine to make your skin sensitive to light) for psoriasis. You may have a higher chance of getting skin cancer while receiving RENFLEXIS.
- have COPD, a specific type of lung disease. Patients with COPD may have an increased risk of getting cancer while receiving RENFLEXIS.
- have or have had a condition that affects your nervous system such as:
  - multiple sclerosis, or Guillain-Barré syndrome, or
  - if you experience any numbness or tingling, or
  - if you have had a seizure.
- have recently received or are scheduled to receive a vaccine. Adults and children receiving RENFLEXIS should not receive live vaccines (for example, the Bacille Calmette-Guérin [BCG] vaccine) or treatment with a weakened bacteria (such as BCG for bladder cancer). Adults and children should have all of their vaccines brought up to date before starting treatment with RENFLEXIS.
- are pregnant or plan to become pregnant, are breastfeeding or plan to breastfeed. You and your doctor should decide if you should receive RENFLEXIS while you are pregnant or breastfeeding.

If you have a baby and you were receiving RENFLEXIS during your pregnancy, it is important to tell your baby's doctor and other health care professionals about your RENFLEXIS use so they can decide when your baby should receive any vaccine. Certain vaccinations can cause infections.
If you received RENFLEXIS while you were pregnant, your baby may be at higher risk for getting an infection. If your baby receives a live vaccine within 6 months after birth, your baby may develop infections with serious complications that can lead to death. This includes live vaccines such as the BCG, rotavirus, or any other live vaccines. For other types of vaccines, talk with your doctor.

How should I receive RENFLEXIS?

- You will be given RENFLEXIS through a needle placed in a vein (IV or intravenous infusion) in your arm.
- Your doctor may decide to give you medicine before starting the RENFLEXIS infusion to prevent or lessen side effects.
- Only a healthcare professional should prepare the medicine and administer it to you.
- RENFLEXIS will be given to you over a period of about 2 hours.
- If you have side effects from RENFLEXIS, the infusion may need to be adjusted or stopped. In addition, your healthcare professional may decide to treat your symptoms.
- A healthcare professional will monitor you during the RENFLEXIS infusion and for a period of time afterward for side effects. Your doctor may do certain tests while you are receiving RENFLEXIS to monitor you for side effects and to see how well you respond to the treatment.
- Your doctor will determine the right dose of RENFLEXIS for you and how often you should receive it. Make sure to discuss with your doctor when you will receive infusions and to come in for all your infusions and follow-up appointments.

What should I avoid while receiving RENFLEXIS?
Do not take RENFLEXIS together with medicines such as KINERET (anakinra), ORENCIA (abatacept), ACTEMRA (tocilizumab), or other medicines called biologics that are used to treat the same conditions as RENFLEXIS.
Tell your doctor about all the medicines you take, including prescription and over-the-counter medicines, vitamins, and herbal supplements. These include any other medicines to treat Crohn's disease, ulcerative colitis, rheumatoid arthritis, ankylosing spondylitis, psoriatic arthritis or psoriasis.
Know the medicines you take. Keep a list of your medicines and show them to your doctor and pharmacist when you get a new medicine.

What are the possible side effects of RENFLEXIS?
RENFLEXIS can cause serious side effects, including:
See "What is the most important information I should know about RENFLEXIS?".
Serious Infections

- Some patients, especially those 65 years and older have had serious infections while receiving infliximab products, such as RENFLEXIS. These serious infections include TB and infections caused by viruses, fungi, or bacteria that have spread throughout the body or cause infections in certain areas (such as skin). Some patients die from these infections. If you get an infection while receiving treatment with RENFLEXIS your doctor will treat your infection and may need to stop your RENFLEXIS treatment.
- Tell your doctor right away if you have any of the following signs of an infection while receiving or after receiving RENFLEXIS:

- a fever
- feel very tired
- have a cough

- have flu-like symptoms
- warm, red, or painful skin

- Your doctor will examine you for TB and perform a test to see if you have TB. If your doctor feels that you are at risk for TB, you may be treated with medicine for TB before you begin treatment with RENFLEXIS and during treatment with RENFLEXIS.
- Even if your TB test is negative, your doctor should carefully monitor you for TB infections while you are receiving RENFLEXIS. Patients who had a negative TB skin test before receiving infliximab products have developed active TB.
- If you are a chronic carrier of the hepatitis B virus, the virus can become active while you are being treated with RENFLEXIS. In some cases, patients have died as a result of hepatitis B virus being reactivated. Your doctor should do a blood test for hepatitis B virus before you start treatment with RENFLEXIS and occasionally while you are being treated. Tell your doctor if you have any of the following symptoms:

- feel unwell
- poor appetite

- tiredness (fatigue)
- fever, skin rash, or joint pain

Heart Failure
If you have a heart problem called congestive heart failure, your doctor should check you closely while you are receiving RENFLEXIS. Your congestive heart failure may get worse while you are receiving RENFLEXIS. Be sure to tell your doctor of any new or worse symptoms including:

- shortness of breath
- swelling of ankles or feet

- sudden weight gain

Treatment with RENFLEXIS may need to be stopped if you get new or worse congestive heart failure.
Other Heart Problems
Some patients have experienced a heart attack (some of which led to death), low blood flow to the heart, or abnormal heart rhythm within 24 hours of beginning their infusion of infliximab products. Symptoms may include chest discomfort or pain, arm pain, stomach pain, shortness of breath, anxiety, lightheadedness, dizziness, fainting, sweating, nausea, vomiting, fluttering or pounding in your chest, and/or a fast or a slow heartbeat. Tell your doctor right away if you have any of these symptoms.
Liver Injury
Some patients receiving infliximab products have developed serious liver problems. Tell your doctor if you have:

- jaundice (skin and eyes turning yellow)
- dark brown-colored urine
- pain on the right side of your stomach area (right-sided abdominal pain)
- fever
- extreme tiredness (severe fatigue)

Blood Problems
In some patients receiving infliximab products, the body may not make enough of the blood cells that help fight infections or help stop bleeding. Tell your doctor if you:

- have a fever that does not go away
- bruise or bleed very easily

- look very pale

Nervous System Disorders
Some patients receiving infliximab products have developed problems with their nervous system. Tell your doctor if you have:

- changes in your vision
- numbness or tingling in any part of your body

- seizures
- weakness in your arms or legs

Some patients have experienced a stroke within approximately 24 hours of their infusion with infliximab products. Tell your doctor right away if you have symptoms of a stroke which may include: numbness or weakness of the face, arm or leg, especially on one side of the body; sudden confusion, trouble speaking or understanding; sudden trouble seeing in one or both eyes, sudden trouble walking, dizziness, loss of balance or coordination or a sudden, severe headache.
Allergic Reactions
Some patients have had allergic reactions to infliximab products. Some of these reactions were severe. These reactions can happen while you are getting your RENFLEXIS treatment or shortly afterward. Your doctor may need to stop or pause your treatment with RENFLEXIS and may give you medicines to treat the allergic reaction. Signs of an allergic reaction can include:

- hives (red, raised, itchy patches of skin)
- difficulty breathing
- chest pain

- high or low blood pressure
- fever
- chills

Some patients treated with infliximab products have had delayed allergic reactions. The delayed reactions occurred 3 to 12 days after receiving treatment with infliximab products. Tell your doctor right away if you have any of these signs of delayed allergic reaction to RENFLEXIS:

- fever
- rash
- headache
- sore throat

- muscle or joint pain
- swelling of the face and hands
- difficulty swallowing

Lupus-like Syndrome
Some patients have developed symptoms that are like the symptoms of Lupus. If you develop any of the following symptoms, your doctor may decide to stop your treatment with RENFLEXIS.

- chest discomfort or pain that does not go away
- shortness of breath

- joint pain
- rash on the cheeks or arms that gets worse in the sun

Psoriasis
Some people receiving infliximab products had new psoriasis or worsening of psoriasis they already had. Tell your doctor if you develop red scaly patches or raised bumps on the skin that are filled with pus. Your doctor may decide to stop your treatment with RENFLEXIS.
The most common side effects of infliximab products include:

- respiratory infections, such as sinus infections and sore throat
- headache

- coughing
- stomach pain

Infusion reactions can happen up to 2 hours after your infusion of RENFLEXIS. Symptoms of infusion reactions may include:

- fever
- chills
- chest pain

- low blood pressure or high blood pressure
- shortness of breath

- rash
- itching

Children with Crohn's disease who received infliximab showed some differences in side effects of treatment compared with adults with Crohn's disease. The side effects that happened more in children were: anemia (low red blood cells), leukopenia (low white blood cells), flushing (redness or blushing), viral infections, neutropenia (low neutrophils, the white blood cells that fight infection), bone fracture, bacterial infection and allergic reactions of the breathing tract. Among patients who received infliximab for ulcerative colitis in clinical studies, more children had infections as compared with adults.
Tell your doctor about any side effect that bothers you or does not go away.
These are not all of the side effects with RENFLEXIS. Ask your doctor or pharmacist for more information.
Call your doctor for medical advice about side effects. You may report side effects to FDA at 1-800-FDA-1088.

General information about RENFLEXIS
Medicines are sometimes prescribed for purposes other than those listed in a Medication Guide.
You can ask your doctor or pharmacist for information about RENFLEXIS that is written for health professionals.

What are the ingredients in RENFLEXIS?
The active ingredient is infliximab-abda.
The inactive ingredients in RENFLEXIS include: dibasic sodium phosphate heptahydrate, monobasic sodium phosphate monohydrate, polysorbate 80, and sucrose. No preservatives are present.
Manufactured by: Samsung Bioepis Co., Ltd., 76, Songdogyoyuk-ro, Yeonsu-gu, Incheon, 21987, Republic of Korea
U.S. License No. 2046
Manufactured for:
Organon LLC, a subsidiary of
ORGANON & Co.,
Jersey City, NJ 07302, USA
The trademarks above are owned by their respective owners.
For more information, go to www.RENFLEXIS.com or call 1-844-674-3200.

This Medication Guide has been approved by the U.S. Food and Drug Administration.

Revised: 10/2025

PRINCIPAL DISPLAY PANEL - 100 mg Vial Carton

NDC 78206-162-01

100
mg/vial

ORGANON

RENFLEXIS®
(infliximab-abda)
for injection

100 mg / vial

For Intravenous Infusion Only

ATTENTION: Dispense the enclosed
Medication Guide to each patient.

Must reconstitute and dilute before
intravenous infusion. Must infuse
over at least 2 hours with
an in-line filter.

One single-dose vial.
Discard unused portion.

Rx only

SAMSUNG BIOEPIS